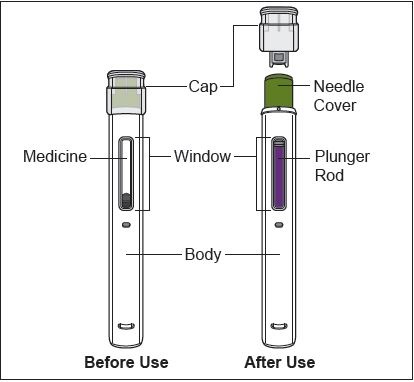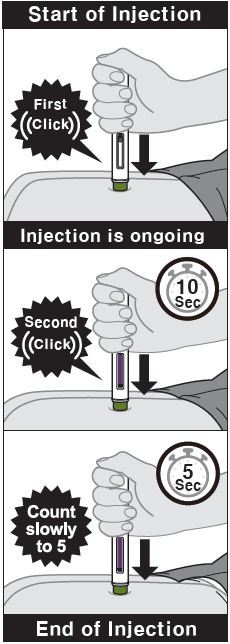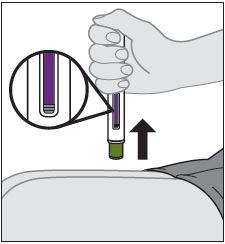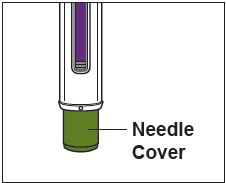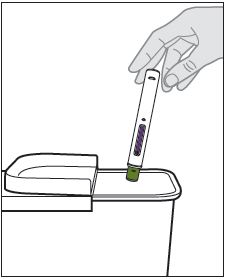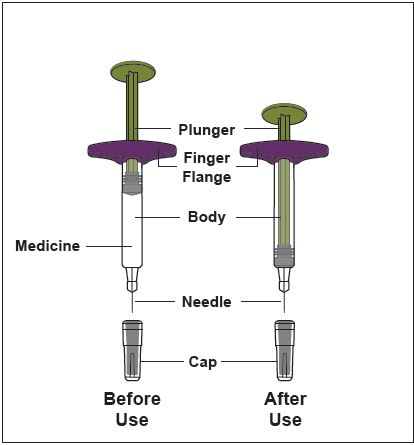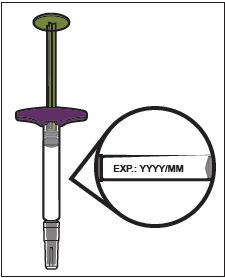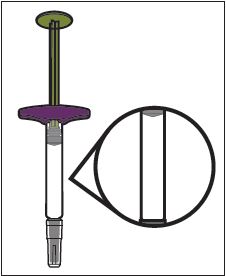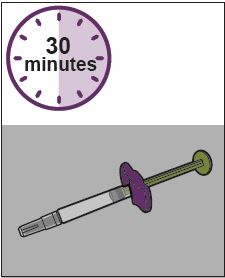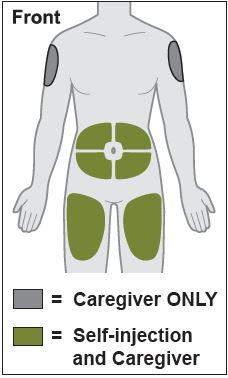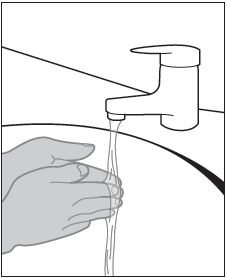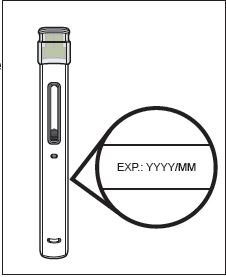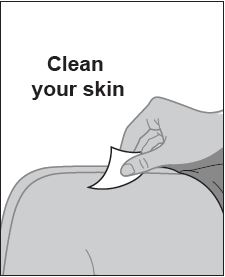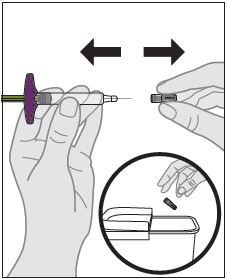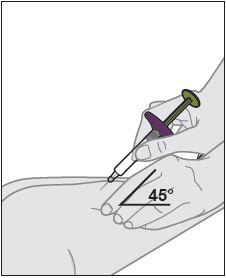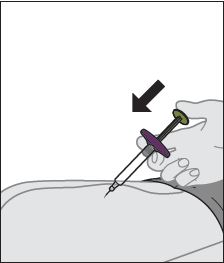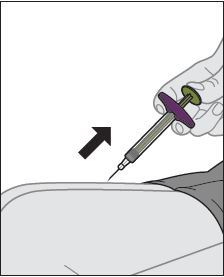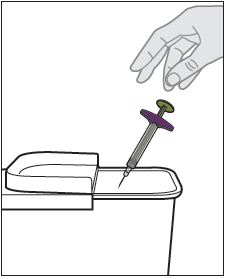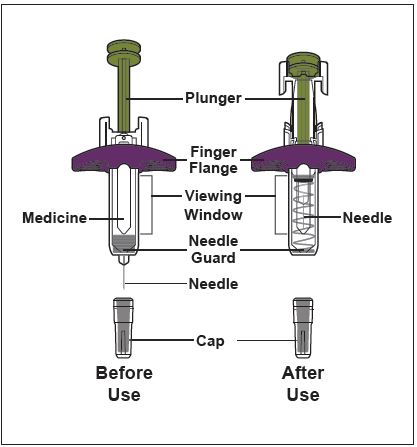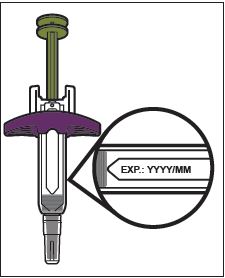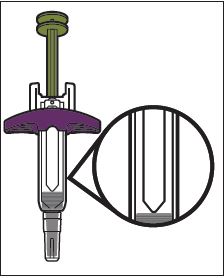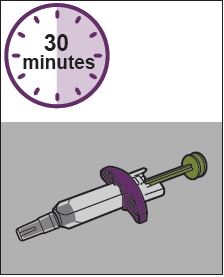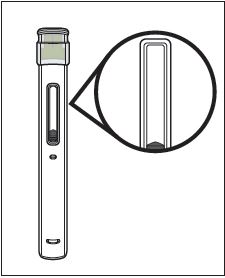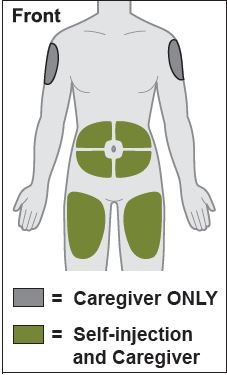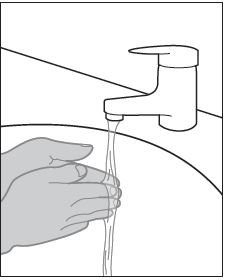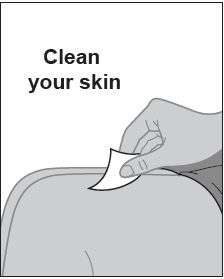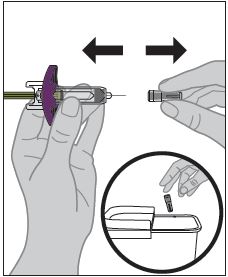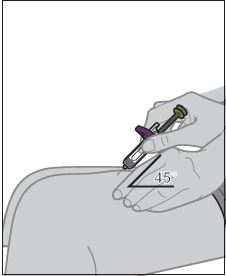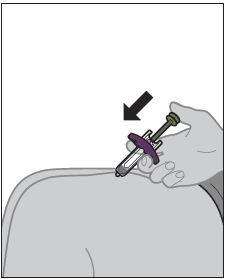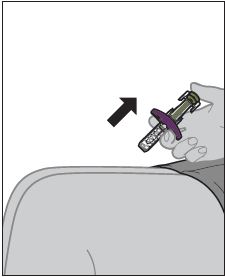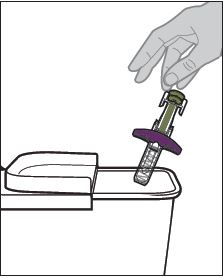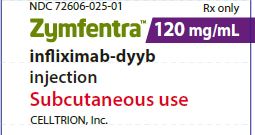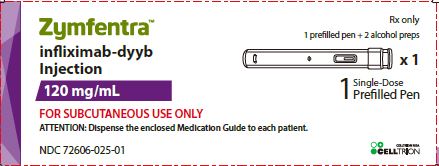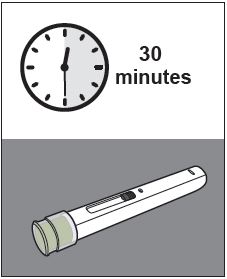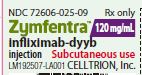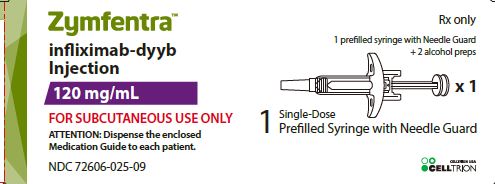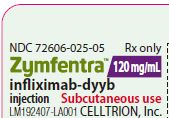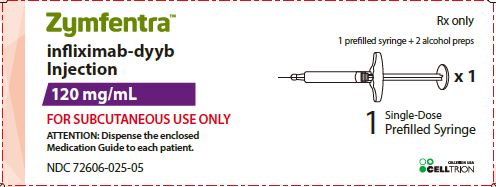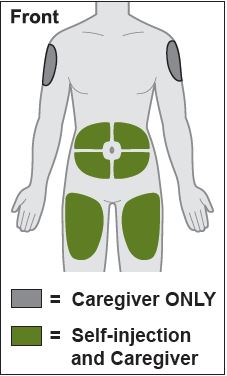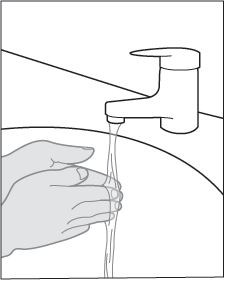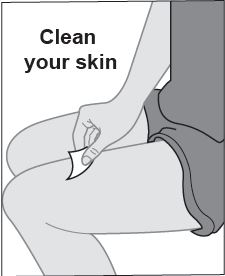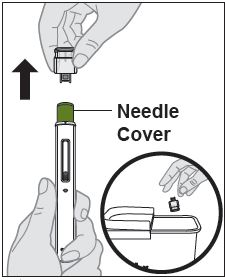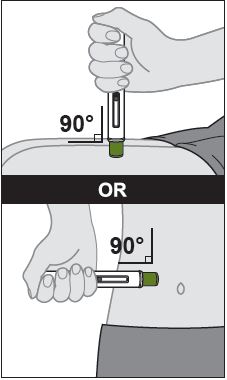 DRUG LABEL: ZYMFENTRA
NDC: 72606-025 | Form: KIT | Route: SUBCUTANEOUS
Manufacturer: CELLTRION USA Inc.
Category: prescription | Type: HUMAN PRESCRIPTION DRUG LABEL
Date: 20250528

ACTIVE INGREDIENTS: INFLIXIMAB-DYYB 120 mg/1 mL; ISOPROPYL ALCOHOL 0.70 mL/1 mL
INACTIVE INGREDIENTS: ACETIC ACID 0.19 mg/1 mL; SODIUM ACETATE 0.56 mg/1 mL; SORBITOL 45 mg/1 mL; POLYSORBATE 80 0.5 mg/1 mL; water

HIGHLIGHTS OF PRESCRIBING INFORMATION

These highlights do not include all the information needed to use ZYMFENTRA safely and effectively. See full prescribing information for ZYMFENTRA.
ZYMFENTRA (infliximab-dyyb) injection, for subcutaneous use
Initial U.S. Approval: 2016

BOXED WARNING

WARNING: SERIOUS INFECTIONS and MALIGNANCY See full prescribing information for complete boxed warning Increased risk of serious infections leading to hospitalization or death, including tuberculosis (TB), bacterial sepsis, invasive fungal infections (such as hitoplasmosis) and infections due to ohter opportunistic pathogens. (5.1) Discontinue ZYMFENTRA if a patient develops a serious infection or sepsis. (5.1) Perform test for latent TB; if positive, start treatment for TB prior to starting ZYMFENTRA. Monitor all patients for active TB during treatment, even if initial latent TB test is negative. (5.1) Lymphoma and other malignancies, some fatal, have been reported in children and adolescent patients treated with tumor necrosis factor (TNF) blockers, including infliximab products. (5.2) Postmarketing cases of fatal hepatosplenic T-cell lymphoma (HSTCL) have been reported in patients treated with TNF blockers including infliximab products. Almost all had received azathioprine or 6-mercaptopurine concomitantly with a TNF blocker at or prior to diagnosis. The majority of cases were reported in patients with Crohn's disease or ulcerative colitis, most of whom were adolescent or young adult males. (5.2)

1 INDICATIONS AND USAGE

ZYMFENTRA is a tumor necrosis factor (TNF) blocker indicated in adults for maintenance treatment of:

- moderately to severely active ulcerative colitis following treatment with an infliximab product administered intravenously. (1)

- moderately to severely active Crohn’s disease following with an infliximab products administered intraneously. (1)

2 DOSAGE AND ADMINISTRATION

Important Dosage Information. (2.1).

- ZYMFENTRA is indicated as maintenance treatment only, starting at Week 10 and thereafter.
  ▫ All pateitns must complete an intravenous induction regiemen with an infliximab product before starting ZYMFENTRA.
- ZYMFENTRA is for subcutaneous use only.

Recommeneded Maintenance Dosage in Ulcerative Colitis and Crohn's Direase (2.2)

- Week 10 and thereafter: Inject 120 mg subcutaneously once every two weeks.
- To swift patients who are responding to maintenance therapy with an infliximab product administered intravenously, administer the first subcutaneous dose of ZYMFENTRA in place of the next scheduled intravenous infusion and every two weeks thereafter.
- See the full prescribing information on how to administer subcutaneously. (2.3)

3 DOSAGE FORMS AND STRENGTHS

Injection (3):

- 120 mg/mL in a single-dose prefilled syringe.
- 120 mg/mL in a single-dose prefilled syringe with needle guard.
- 120 mg/mL in a single-dose prefilled pen.

4 CONTRAINDICATIONS

- History of severe hypersentitivity reaction to infliximab-dyyb, other infliximab products, any of the inactive ingredients in ZYMFENTRA or to any murine proteins. (4)

5 WARNINGS AND PRECAUTIONS

- Serious injections, including invasive fungal infections: Avoid use of ZYMFENTRA in patients with an active infection. If infection develops during treatment, conduct a prompt and complete diagnostic workup appropriate for an immunocompromised patient and initiate antimicrobial therapy. If systemic illness develops in patients who reside or travel to regions where mycoses are endemic, consider empiric antifungal therapy. (5.1)
- Malignancies: The incidence of malignancies, including lymphoma, was greater in TNF blocker-treated patients than in controls. Consider the higher risk of hepatosplenic T-cell lymphoma (HSTCL) with combination therapy versus increased tisk of immunogenicity and hypersensitivity reactions with monotherapy. (5.2)
- Hepatitis B virus (HBV) reactivation: Test for HBV infection before starting ZYMFENTRA. Monitor HBV carriers during and several months after therapy for active HBV infection. If reactivation occurs, stop ZYMFENTRA and begin anti-viral therapy. (5.3)
- Hepatotoxicity: Severe hepatic reactions, some fatal or necessitating liver transplantation with infliximab products. Monitor hepatic enzymes and liver function tests every 3 to 4 months during treatment; investigate liver enzyme elevations and interrupt treatment if drug-induced liver injury is suspected. Instruct patients to seek immediate medical attention if symptoms develop. (5.4)
- Congestive heart failure (CHF): New onset or worsening symptoms may occur. Avoid ZYMFENTRA in patients with CHF. Monitor for new or worsening symptoms if a decision is made to administer ZYMFENTRA. (5.5)
- Hematologic Reactions: Advise patients to seek immediate medical attention if signs and symtoms of cytopenia develop; consider stopping ZYMFENTRA if significant hematologic abnormalities devlop. (5.6)
- Hypersensitivity and Other Administration Reactions: Serious systemic hypersensitivity reactions including anaphylaxis; institute appropriate therapy and discontinue ZYMFENTRA. (4, 5.7)
- Neurologic Reactions: Exacerbation or new onset CNS demyelinating disorders may occurs; consider discontinuation of ZYMFENTRA. (5.8)
- Risk of infection with concurrent administration of other biological products: Concurrent use with other immunosuppressive biological products may increase the risk of injection (5.9)
- Risk of additive immunosuppressive effects from prior biologic products: Consider the half-life and mode of action of prior biological products. (5.10)
- Autoimmunity: Formation of autoantibodies and development of lupus-like syndrome may occur; discontinue ZYMFENTRA if symptoms develop. (5.11)
- Vaccinations and Use of Live Vaccines/Therapeutic Infectious Agents: Prior to initiating ZYMFENTRA bring patients up to date with all vaccinations. Live vaccines or therapeutic infectious agents should not be given with ZYMFENTRA. A 6-month waiting period following birth is recommended before the administration of live vaccines to infants exposed in utero to infliximab products. (5.12)

6 ADVERSE REACTIONS

Most common adverse reactions (>3%) are:

- Ulcerative Colitis: COVID-19, anemia, arthralgia, injection site reaction, increased alanine aminotransferase, and abdominal pain. (6.1)
- Crohn's Disease: COVID-19, headache, upper respiratory tract infection, injection site reaction, diarrhea, increased blood creatine phosphokinase, arthralgia, increased alanine aminotransferase, hypertension, urinary tract infection, neutropenia, dizziness, and leukopenia. (6.1)

To report SUSPECTED ADVERSE REACTIONS, contact CELLTRION USA, Inc. at 1-800-560-9414 or FDA at 1-800-FDA-1088 or www.fda.gov/medwatch.

FULL PRESCRIBING INFORMATION

BOXED WARNING

SERIOUS INFECTIONS

Patients treated with TNF blockers, inculding ZYMFENTRA, are at increased risk for developing serious infections that may lead to hospitalization or death [see Warnings and Precautions (5.1), Adverse Reactions (6.1)]. Most patients who developed these infections were taking concomitant immunosuppressants such as methotrexate or corticosteroids.

Discontinue ZYMFENTRA if a patient develops a serious infection or sepsis.

Reported infections include:

- Active tuberculosis, including reactivation of latent tuberculosis. Patients with tuberculosis have frequently presented with disseminated or extrapulmonary disease. Test patientsfor latent tuberculosis before ZYMFENTRA use and during therapy. Initiate treatment for latent infection prior to ZYMFENTRA use.
- Invasive fungal infections, including histoplasmosis, coccidioidomycosis, candidiasis, aspergillosis, blastomycosis, and pneumocystosis. Patients with histoplasmosis or other invasive fungal infections may present with disseminated, rather than localized, disease. Antigen and antibody testing for histoplasmosis may be negative in some patients with active infection. Consider empiric anti-fungal therapy in patients at risk for invasive fungal infections who develop severe systemic illness.
- Bacterial, viral and other infections due to opportunistic pathogens, including Legionella and Listeria.

Carefully consider the risks and benefits of treatment with ZYMFENTRA prior to initiating therapy in patients with chronic or recurrent infection.

Closely monitor patients for the development of signs and symtoms of infection during and after treatment with ZYMFENTRA, including the possible development of tuberculosis in patients who tested negative for latent tuberculosis infection prior to initiating therapy.

MALIGNANCY

Lymphoma and other malignancies, some fatal, have been reported in children and adolescent patients treated with TNF blockers, including infliximab products [see Warnings and Precautions (5.2)].

Postmarketing cases of hepatosplenic T-cell lymphoma (HSTCL), a rare type of T-cell lymphoma, have been reported in patients treated with TNF blockers, including infliximab products. These cases have had a very aggressive disease course and have been fatal. Almost all patients had received treatment with azathioprine or 6-mercaptopurine concomitantly with a TNF blocker at or prior to diagnosis. The majority of reported cases have occurred in patients with Crohn’s disease or ulcerative colitis and most were in young adult males. [see Use in Specific Population (8.4)].

1 INDICATIONS AND USAGE

ZYMFENTRA is indicated in adults for maintenance treatment of:

- moderately to severely active ulcerative colitis following treatment with an infliximab product administered intravenously.
- moderately to severely active Crohn's disease following treatment with an infliximab product administered intravetnously.

2 DOSAGE AND ADMINISTRATION

2.1 Important Dosage Information

- ZYMFENTRA is indicated as maintenance treatment only, starting at Week 10 and thereafter.▫ All patients mush coplete an intravenous induction regimen with an infliximab product before starting ZYMFENTRA. For induction dosing information, see the corresponding full prescribing information for the chosen infliximab product.
- ZYMFENTRA is for subtutaneous use only.

2.2 Recommeneded Dosage for Maintenance Treatment in Ulcerative Colitis Crohn's Disease

- Maintenance dosage starting at Week 10 and thereafter: 120 mg subcutaneously once every two weeks. To switch patients who are responding to maintenance therapy with an infliximab product administered intravenously, administer the first subcutaneous dose of ZYMFNETRA in place of the next scheuled intravenous infusion and every two weeks thereafter.

2.3 Subcutaenous Administration Instructions

- ZYMFENTRA is intended for use under the guidance and supervision of a healthcare professional.
- If a healthcare professional determines that it is appropriate, patients may self-injection ZYMFENTRA or caregivers may injection ZYMFENTRA using either the ZYMFENTRA prefilled syringe, ZYMFENTRA prefilled syringe with needle guard, or ZYMFENTRA prefilled pen after proper training in subcutaenous injection technique.
- Parental drug products should be inspected visually for particulate matter and discoloration prior to administration, whether solution and container permit. ZYMFENTRA should be a clear, colorless to pale brwon solution. Do not use if particulates or discoloration is presnet.
- Inject into the front of the tights, the abdomen excepts for the 2 inches around the navel, or the outer area of the upper arms (caregiver only).
- Rotate the injectoin site each time an inejction is given. Allow at least 1.2 inches between the new injection site and the previous inejction site. Never inject into areas where the skin is red, bruised, tender, or indurated.
- Do not use the syringe or pen of it has been dropped or is visibly damaged. A damaged syringe may not function proprely.
- Do not resue or shake the syringe or pen at any time.

Mixed Dose

If an injection of ZYMFENTRA is missed, inject the next subcutaneous dose as soon as possible and then every two weeks thereafter.

3 DOSAGE FORMS AND STRENGTHS

ZYMFENTRA (infliximab-dyyb) is a clear, colorless to pale brown solution available as follow:

- Injection: 120 mg/mL in a single-dose prefilled syringe.
- Injection: 120 mg/mL in a single-dose prefilled syringe with needle guard.
- Injection: 120 mg/mL in a single-dose prefilled pen.

4 CONTRAINDICATIONS

ZYMFENTRA is contraindicated in patients with a history of a severe hypersensitivity reaction to infliximab-dyyb, other infliximab products, any of the inactive ingredients in ZYMFENTRA, or any murine proteins. Reactions have included anaphylaxis [see Warnings and Precautions (5.7)].

5 WARNINGS AND PRECAUTIONS

5.1 Serious Infections

Patients treated with ZYMFENTRA are at increased risk for developing serious infections involving various organ systems and sites that may lead to hospitalization or death.

Opportunistic infections due to bacterial, mycobacterial, invasive fungal, viral, or parasitic organisms including aspergillosis, blastomycosis, candidiasis, coccidioidomycosis, cryptococcosis, histoplasmosis, legionellosis, listeriosis, pneumocystosis, salmonellosis and tuberculosis have been reported with TNF blockers. Patients have frequently presented with disseminated rather than localized disease.

Treatment with ZYMFENTRA should not be initiated in patients with an active infection, including clinically important localized infections.Patients greater than 65 years of age, patients with comorbid-conditions and/or patients taking concomitant immunosuppressants such as corticosteroids or methotrexate may be at greater risk of infection. The risks and benefits of treatment should be considered prior to initiating therapy in patients:

- with chronic or recurrent infection;
- who have been exposed to tuberculosis;
- with a history of an opportunistic infection;
- who have resided or traveled in areas of endemic tuberculosis or endemic mycoses, such as histoplasmosis, coccidioidomycosis, or blastomycosis; or
- with underlying conditions that may predispose them to infection.

Tuberculosis

Cases of reactivation of tuberculosis or new tuberculosis infections have been observed in patients receiving TNF-blockers, including patients who have previously received treatment for latent or active tuberculosis. Cases of active tuberculosis have also occurred in patients being treated with infliximab products during treatment for latent tuberculosis. Evaluate patients for tuberculosis risk factors and test for latent infection prior to initiating ZYMFENTRA and periodically during therapy.

Treatment of latent tuberculosis infection prior to therapy with TNF blockers has been shown to reduce the risk of tuberculosis reactivation during therapy. Induration of 5 mm or greater with tuberculin skin testing should be considered a positive test result when assessing if treatment for latent tuberculosis is needed prior to initiating ZYMFENTRA even for patients previously vaccinated with Bacille Calmette-Guérin (BCG).

Consider anti-tuberculosis therapy prior to initiation of ZYMFENTRA in patients with a past history of latent or active tuberculosis in whom an adequate course of treatment cannot be confirmed, and for patients with a negative test for latent tuberculosis but having risk factors for tuberculosis infection. Consultation with a physician with expertise in the treatment of tuberculosis is recommended to aid in the decision whether initiating anti-tuberculosis therapy is appropriate for an individual patient.

Tuberculosis should be strongly considered in patients who develop a new infection during treatment with ZYMFENTRA especially in patients who have previously or recently traveled to countries with a high prevalence of tuberculosis, or who have had close contact with a person with active tuberculosis.

Monitoring

Closely monitor patients for the development of signs and symptoms of infection during and after treatment with ZYMFENTRA including the development of tuberculosis in patients who tested negative for latent tuberculosis infection prior to initiating therapy. Tests for latent tuberculosis infection may also be falsely negative while on therapy with ZYMFENTRA.

Discontinue ZYMFENTRA if a patient develops a serious infection or sepsis. A patient who develops a new infection during treatment with ZYMFENTRA should undergo prompt and complete diagnostic workup appropriate for an immunocompromised patient; and appropriate antimicrobial therapy should be initiated, and the patient should be closely monitored.

Invasive Fungal Infections

For patients who reside or travel in regions where mycoses are endemic, invasive fungal infection should be suspected if they develop a serious systemic illness. Appropriate empiric antifungal therapy should be considered while a diagnostic workup is being performed. Antigen and antibody testing for histoplasmosis may be negative in some patients with active infection. When feasible, the decision to administer empiric antifungal therapy in these patients should be made in consultation with a physician with expertise in the diagnosis and treatment of invasive fungal infections and should take into account both the risk for severe fungal infection and the risks of antifungal therapy.

5.2 Malignancies

Malignancies, some fatal, have been reported among children, adolescents and young adults who received treatment with TNF blockers (initiation of therapy ≤18 years of age), including infliximab products. AApproximately half of these cases were lymphomas, including Hodgkin’s and non-Hodgkin’s lymphoma. The other cases represented a variety of malignancies, including rare malignancies that are usually associated with immunosuppression and malignancies that are not usually observed in children and adolescents. The malignancies occurred after a median of 30 months (range 1 to 84 months) after the first dose of TNF blocker therapy. Most of the patients were receiving concomitant immunosuppressants. These cases were reported postmarketing and are derived from a variety of sources, including registries and spontaneous postmarketing reports.

Lymphomas

In the controlled portions of clinical trials of TNF blockers, more cases of lymphoma have been observed among patients receiving a TNF blocker compared with control patients. Cases of acute and chronic leukemia have been reported with postmarketing TNF blocker use, including infliximab products.

Hepatosplenic T-cell Lymphoma (HSTCL)

Postmarketing cases of hepatosplenic T-cell lymphoma (HSTCL), a rare type of T-cell lymphoma, have been reported in patients treated with TNF blockers, including infliximab products. TThese cases have had a very aggressive disease course and have been fatal. Almost all patients had received treatment with the immunosuppressants azathioprine or 6-mercaptopurine concomitantly with a TNF blocker at or prior to diagnosis. The majority of reported cases have occurred in patients with Crohn’s disease or ulcerative colitis and most were in adolescent and young adult males. It is uncertain whether the occurrence of HSTCL is related to TNF blockers or TNF blockers in combination with these other immunosuppressants. When treating patients, consideration of whether to use ZYMFENTRA alone or in combination with other immunosuppressants such as azathioprine or 6-mercaptopurine should take into account a possibility that there is a higher risk of HSTCL with combination therapy versus an observed increased risk of immunogenicity and hypersensitivity reactions with TNF blocker monotherapy from the clinical trial data [see Warnings and Precautions (5.7)]

Skin Cancer

Melanoma and Merkel cell carcinoma have been reported in patients treated with TNF blocker therapy, including infliximab products. Periodic skin examination is recommended for all patients during treatment with ZYMFENTRA, particularly those with risk factors for skin cancer.

Cervical Cancer

Cases of invasive cervical cancer have been reported postmarketing in women who received infliximab products for other conditions. A causal relationship between infliximab products and cervical cancer cannot be excluded. Routine cervical cancer screening is recommended during treatment with ZYMFENTRA.

Other Malignancies

In the controlled pportions of clinical trials of some TNF blockers, including infliximab products, more malignancies (excluding lymphoma and nonmelanoma skin cancer) have been observed in patients receiving those TNF blockers compared with control patients. The most common malignancies were breast, colorectal, and melanoma in these controlled trials of TNF blockers.

In controlled trials of TNF blockers in adult patients at higher risk for malignancies (i.e., patients with COPD with a significant smoking history and cyclophosphamide-treated patients with Wegener’s granulomatosis), a greater proportion of malignancies occurred in the TNF blocker group compared to the control group. Patients had a history of heavy smoking. Avoid ZYMFENTRA in patients with moderate to severe COPD.

The potential role of TNF blockers in the development of malignancies is not known. Avoid ZYMFENTRA treatment in patients with a history of malignancy or in continuing treatment in patients who develop malignancy while receiving ZYMFENTRA.

5.3 Hepatitis B Virus Reactivation

Use of TNF blockers has been associated with reactivation of hepatitis B virus (HBV) in patients who are chronic carriers of this virus. In some instances, HBV reactivation occurring in conjunction with TNF blocker therapy has been fatal. The majority of these reports have occurred in patients concomitantly receiving other medications that suppress the immune system, which may also contribute to HBV reactivation.

Test patients for HBV infection before initiating TNF blocker therapy, including ZYMFENTRA. For patients who test positive for hepatitis B surface antigen, consultation with a physician with expertise in the treatment of hepatitis B is recommended. Adequate data are not available on the safety or efficacy of treating patients who are carriers of HBV with antiviral therapy in conjunction with TNF blocker therapy to prevent HBV reactivation. Patients who are carriers of HBV and require treatment with TNF blockers, including ZYMFENTRA, should be closely monitored for clinical and laboratory signs of active HBV infection throughout therapy and for several months following termination of therapy.

In patients who develop HBV reactivation, discontinue ZYMFENTRA and initiate antiviral therapy with appropriate supportive treatment. The safety of resuming TNF blocker therapy after HBV reactivation is controlled is not known. Therefore, prescribers should exercise caution when considering resumption of ZYMFENTRA in this situation and monitor patients closely.

5.4 Hepatotoxicity

Hepatobiliary disorders, including acute liver failure, jaundice abnormal hepatic function, hepatic steatosis, hepatitis, hepatotoxicity, hyperbilirubinemia and non-alcoholic fatty liver, have been reported in postmarketing data in patients receiving infliximab products. Autoimmune hepatitis has been diagnosed in some of these cases. Severe hepatic reactions occurred between two weeks to more than one year after initiation of infliximab products administered intravenously; elevations in hepatic aminotransferase levels were not noted prior to discovery of the liver injury in many of these cases. Some of these cases were fatal or necessitated liver transplantation.

In clinical trials, three subjects treated with ZYMFENTRA had drug induced liver injury based on hepatic transaminase elevations, including one subject with accompanying bilirubin elevation [see Adverse Reactions (6.2)].

Monitor hepatic enzymes and liver function tests every 3 to 4 months during treatment with ZYMFENTRA. Prompt investigation of the cause of liver enzyme elevation should be undertaken to identify potential cases of drug-induced liver injury. Interrupt treatment if drug-induced liver injury is suspected, until this diagnosis is excluded. Instruct patients to seek immediate medical attention if they experience symptoms suggestive of hepatic dysfuction.

5.5 Congestive Heart Failure

Cases of worsening congestive heart failure (CHF) and new onset CHF, with and without identifiable precipitating factors (e.g., pre-existing cardiovascular disease), have been reported with TNF blockers, including infliximab products. Some of these patients have been under 50 years of age, and some cases had a fatal outcome. In several exploratory trials of other TNF blockers in the treatment of CHF, there were greater proportions of TNF-blocker-treated patients who had CHF exacerbations requiring hospitalization or increased mortality. ZYMFENTRA has not been studied in patients with a history of CHF. Avoid ZYMFENTRA in patients with CHF.

If a decision is made to administer ZYMFENTRA to patients with CHF, closely monitor patients during therapy for new or worsening symptoms of heart failure and discontinue ZYMFENTRA if symptoms appear.

5.6 Hematologic Reactions

Report of pancytopenia including aplastic anemia have been reported with TNF blocking agents. Cases of leukopenia, neutropenia, thrombocytopenia, and pancytopenia, some with a fatal outcome, have been reported in patients receiving infliximab products. Clinically significant events of neutropenia were noted in the clinical trials of ZYMFENTRA. The causal relationship to infliximab product therapy remains unclear. Although no high-risk group(s) has been identified, avoid ZYMFENTRA in patients who have ongoing or a history of significant hematologic abnormalities. Advise all patients to seek immediate medical attention if they develop signs and symptoms suggestive of blood dyscrasias or infection (e.g., persistent fever) during treatment with ZYMFENTRA. Consider discontinuation of ZYMFENTRA therapy in patients who develop significant hematologic abnormalities.

5.7 Hypersensitivity and Other Administration Reactions

In clinical trials of ZYMFENTRA, symptoms compatible with hypersensitivity reactions have been reported including bronchospasm, dyspnea, rash, and edema. In post-marketing experience, serious systemic hypersensitivity reactions (including anaphylaxis, hypotension, and serum sickness) have been reported following administration of infliximab products. If an anaphylactic or other clinically significant hypersensitivity reaction occurs, institute appropriate therapy and discontinue ZYMFENTRA. There are no data on the risks of using ZYMFENTRA in patients who have experienced a severe hypersensitivity reaction towards another TNF blocker; in these patients, caution is needed.

5.8 Neurologic Reactions

Agents that inhibit TNF have been associated with central nervous system (CNS) manifestation of systemic vasculitis, seizure and new onset or exacerbation of clinical symptoms and/or radiographic evidence of CNS demyelinating disorders, including multiple sclerosis and optic neuritis, and peripheral demyelinating disorders, including Guillain-Barré syndrome. Avoid the use of ZYMFENTRA in patients with these neurologic disorders and consider discontinuation of ZYMFENTRA if these disorders develop.

5.9 Risk of Infection with Concurrent Administration with Other Biological Products

Serious infections and neutropenia have been reported with concurrent use of TNF-blockers and other immunosuppressive biological products (e.g., anakinra and abatacept). The concurrent use of ZYMFENTRA with other immunosuppressive biological products used to treat ulcerative colitis and Crohn’s disease may increase the risk of infection and is not recommended [see Drug Interactions (7.1)].

5.10 Risk of Additive Immunosuppressive Effects from Prior Biological Products

Consider the half-life and mode of action of prior biological products to avoid unintended additive immunosuppressive effects when initiating ZYMFENTRA [see Drug Interactions (7.1)].

5.11 Autoimmunity

Treatment with TNF blockers, iincluding ZYMFENTRA may result in the formation of autoantibodies and in the development of a lupus-like syndrome. If a patient develops symptoms suggestive of a lupus-like syndrome following treatment with ZYMFENTRA, discontinue treatment.

5.12 Vaccinations and Use of Live Vaccines/Therapeutic Infectious Agents

Vaccinations

Prior to initiating ZYMFENTRA in adult patients, update vaccinations in accordance with current vaccination guidelines.

Live Vaccines and Theraeputic Infectious Agents

In patients receiving TNF blockers, limited data are available on the response to vaccination with live vaccines or on the secondary transmission of infection by live vaccines. Use of live vaccines can result in clinical infections, including disseminated infections. The concurrent administration of live vaccines with ZYMFENTRA is not recommended.

Fatal outcome due to disseminated BCG infection has been reported in an infant who received a BCG vaccine after in utero exposure to infliximab products. Infliximab is known to cross the placenta and has been detected in the serum of infants up to 6 months following birth. A 6-month waiting period following birth is recommended before the administration of any live vaccine to infants exposed in utero to infliximab products.

Other uses of therapeutic infectious agents such as live attenuated bacteria (e.g., BCG bladder instillation for the treatment of cancer) could result in clinical infections, including disseminated infections. It is recommended that therapeutic infectious agents not be given concurrently with ZYMFENTRA.

6 ADVERSE REACTIONS

The following clinically significant adverse reactions are described elsewhere in the labeling:

- Serious infections [see Warnings and Precautions (5.1)]
- Malignancies [see Warnings and Precautions (5.2)]
- Hepatitis B virus reactivation [see Warnings and Precautions (5.3)]
- Hepatotoxicity [see Warning and Precautions (5.4)]
- Congestive heart failure [see Warnings and Precautions (5.5)]
- Hematologic reactions [see Warnings and Precautions (5.6)]
- Hypersensitivity and other administration reactions [see Warnings and Precautions (5.7)]
- Neruologic reactions [see Warnings and Precautions (5.8)]
- Autoimmunity [see Warnings and Precautions (5.11)]

6.1 Clinical Trials Experience

- Because clinical trials are conducted under widely varying conditions, adverse reaction rates observed in the clinical trials of a drug cannot be directly compared to rates in the clinical trials of another drug and may not reflect the rates observed in practice.
- The data described below reflect exposure to ZYMFENTRA in 518 adult subjects in two 54-weekrandomized, double-blind, placebo-controlled trials in subjects with moderately to severely active ulcerative colitis (UC) or Crohn’s disease (CD) (UC Trial I an CD Trial I). Subject who achieved clinical response following three induction doses of infliximab-dyyb administered as an intravenous infusion at Week 0, 2 and 6 were randomized 2:1 to ZYMFENTRA 120 mg or placebo as a subcutaneous injection every two weeks at Week 10 [see Clinical Studies (14.1 and 14.2)].

Ulcerative Colitis

The most common adverse reactions reported in ≥3% of subjects and at a higher rate than Placebo in UC Trial I are shown in Table 1.

Table 1 Adverse Reactionsa in the Maintenance Phase of a Randomized, Double-Blind 54-Week Study of Subjects with UC (UC Tral I)
 | ZYMFENTRA; 120 mg Subcutaneous; Injectionb; N=296; (%) | Placebo; N=140; (%)
COVID-19 | 10 | 6
Anemiad | 5 | 4
Arthralgia | 4 | 1
Injection site reaction# | 3 | 2
Increased alanine aminotransferase | 3 | 1
Abominal painf | 3 | 1
areported in at least 3% of ZYMFENTRA-treated subjects and at a higher than placebo
bZYMFENTRA 120 mg as a subcutaneous injection every two weeks starting Week 10 following 3 intravenous induction doses of inflixiab-dyyb
cIncludes: COVID-19 and COVID-19 pneumonia
dIncludes: anemia and iron deficiency anemia
#Some subjects had multiple occurences of injection site reactions. In this table, injection site reactions are counted only once per subject. Symptoms in individual subjects included one or more of injection site bruising, edema, erythema, induration, pain, pruritus and swelling.
fIncludes: abdominal pain, upper abdominal pain, lower abdominal pain, and abdominal discomfort

Crohn's Disease

The most common adverse reactions reported in ≥3% of subjects and at a higher rate than placebo in CD Trial I are shown in Table 2.

Table 2 Adverse Reactionsa in the Maintenance Phase of a Randomized, Double-Blind
54-Week Study of Subjects with CD (CD Trial I)
 | ZYMFENTRA; 120 mg Subcutaneous; Injectionb; N=222; (%) | Placebo; N=101; (%)
COVID-19 | 10 | 5
Headache | 8 | 4
Upper respiratory track infectionsdc | 7 | 3
Injection site reactiond | 5 | 1
Diarrhea | 5 | 1
Increased blood creatine phosphokinase | 4 | 2
Arthralgia | 4 | 3
Increased alaine aninotransferase | 4 | 1
Hypertensionse | 3 | 2
Urinary track infectionf | 3 | 2
Neutropenia | 3 | 0
Dizziness | 3 | 0
Leukopenia | 3 | 0
a reported in at least 3% of ZYMFENTRA-treated subjects and at a higher rate than placebo
b ZYMFENTRA 120 mg administered subcutaneously starting at Week 10 and every 2 weeks thereafter for up to Week 54.
c Includes: upper respiratory tract infection, acute sinusitis, chronic sinusitis, influenza like illness, nasopharyngitis, pharyngitis, pharyngitis streptococcal, rhinitis, rhinorrhea, rhinovirus infection, sinusitis, tonsillitis
d Some subjects had multiple occurrences of injection site reactions. In this table, injection site reactions are counted only once per subject. Symptoms in individual subjects included one or more of injection site bruising, edema, erythema, induration, pain, pruritus, rash, swelling, warmth.
e Includes: hypertension and essential hypertension
f Includes: urinary tract infection, pyelonephritis

Adverse Evetns of Special Interest

Infections

In UC Trial I, at leaset one serious infection was reported in 3% of ZYMFENTRA-treated subjects compared to 1% in the plaebo group. Serious infections in the ZYMFENTRA-treated subjects were COVID-19, cystitis, pneumonia, salpingitis, and urinary tract injection [see Warnings and Precautions (5.1)].

In CD Trial I, infections were observed in 30% of ZYMFENTRA-treated subjects compare to 187% of placebo-treated subjects. At least one serious infection was reported in 3% of ZYMFENTRA-treated subjects compared to 1% in the placebo group. Serious infections in the ZYMFENTRA-treated subjects were abscess, appendicitis, bacterial arthritis, bartholinitis, bronchiolitis, and urinary tract infection [see Warnings and Precautions (5.1)].

Malignancies

In UC Trial I, malignancy (prostate cancer) was reported in a ZYMFENTRA-treated subject. No malignancies were reported among placebo-treated subjects [see Warnings and Precautions (5.2)].

In another clinical trial in patients with CD, one malignancy (non-small cell lung cancer) was reported in a ZYMFENTRA-treated subject [see Warnings and Precautions (5.2)].

Hepatotoxicity

Three cases of drug induced liver injury were noted in ZYMFENTRA-treated subjects that led to study drug discontinuation [see Warnings and Precautions (5.4)].

- In two subjects in UC Trial I, ALT and AST levels started rising 7 to 12 months after starting ZYMFENTRA, reaching peak values of 4 to 11x ULN for ALT, and 2 to 7x ULN for AST. Inboth subjects, total bilirubin levels remains below 2x ULN.
- In one subject in CD Trial I, ALT and AST started rising within a month after starting ZYMFENTRA, reaching peack values of 18x ULN for ALT and 14.9x ULN for AST. At approximately 5 months, total bilirubin level also increased to a peak value of 2.5x ULN.

6.2 Postmarketing Experience

The following adverse reactions have been identified during post-approval use of outside of the U.S with a non-U.S approved infliximab product administered subcutaneously. Because these reactions are reported voluntarily from a population of uncertain size, it is not always possible to reliably estimate their frequency or establish a causal relationship to drug exposure.

- Infections and infestations: cellulitis, disseminated tuberculosis, lower respiratory tract infection, pneumonia, sepsis
- Neoplasms benign, malignant and unspecified: breast cancer, gastric cancer, lung cancer
- Nervous system disorders: multiple sclerosis
- General disorders and administration site conditions: fatigue, malaise

The following additional adverse ractions have been identified during post-approval use of infliximab products administered intravenously.

- Neutropenia, agranuloxytosis (including infants exposed in utero to infliximab products), idiopathis thrombocytopenic purpura, thrombotic thrombocytopenic purpura.
- Interstitial lung disease (including pulmonary fibrosis/interstitial pneumonitis and rapidly progessive disease).
- Pericardial effusion, systemic and cutaneous vasculitis.
- Erythema multiforme, Stevens-Johnson Syndrome, toxic epidermal necrolysis, linear IgA bullous dermatosis (LABD), acute generalized exanthematous pustulosis (AGEP), new onset and worsening psoriasis (all subtypes including pustular, primarily palmoplantar), lichenoid react.
- Preipheral demyelinating disorders (such as Guillain-Barré syndrome, chronic inflammatory demyelinating polyneuropathy, and multifocal motor neuropathy) transverse myelitis, and neuropathies (additional neurologic reactions have also been observed).
- Acute liver failure, jaundice, hepatitis, and cholestasis.
- Serious infections and vaccine breakthrough infection including bovine tuberculosis (disseminated BCG infection) following vaccination in an infant exposed in utero to infliximab products.
- Malignancies, including leukemia, melanoma, Merkel cell carcinoma, and cervical cancer.
- Anaphylactic reactions, including anaphylactic shock, laryngeal/pharyngeal edema and severe bronchospasm, and seizure.
- Transient visual loss has been reported in association with infliximab products during or within 2 hours of infusion. Cerebrovascular accidents, myocardial ischemia/infarction (some fatal), and arrhythmia occurring within 24 hours of initiation of infusion have also been reported.

7 DRUG INTERACTIONS

7.1 Other Biological Products Used to Treat UC and CD

The concurrent use of ZYMFENTRA with other immunosuppressive biological products used to treat UC and CD may increase the risk of infection and is not recommended [see Warnings and Precautions (5.9)].

Consier the half-life and mode of action of prior biologial products to avoid unintended additive immunosuppressive effects when initiating ZYMFENTRA [see Warnings and Precautions (5.10)].

7.2 Cytochrome P450 Substrates

The formation of CYP450 enzymes may be suppressed by increased levels of cytokines (e.g., TNFα, IL-1, IL-6, IL-10, IFN) during chronic inflammation. Therefore, ZYMFENTRA, an antagonist of TNFα, could normalize the formation of CYP450 enzymes potentially resulting in a decrease in exposure of CYP450 substrates.

Upon initiation or discontinuation of TNF blockers, including ZYMFENTRA, in patients being treated with CYP450 substrates requiring therapeutic drug monitoring, monitor therpeutic parameters (e.g., INR for warfarin) or drug concentration (e.g., cyclosporine or theophylline). Dosage adjustment may be needed to maintain drug concentrations or parameters within the therapeutic range. See prescribing information for specific drugs.

7.3 Live Vaccines/Therapeutic Infectious Agents

It is recommended that live vaccines not be given concurrently with ZYMFENTRA. It is also recommended that live vaccines not be given to infants after in utero exposure to infliximab products for 6 months following birth [see Warnings and Precautions (5.12)].

It is recommended that therapeutic infectious agents not be given concurrently with ZYMFENTRA [see Warnings and Precautions (5.12)].

8 USE IN SPECIFIC POPULATIONS

8.1 Pregnancy

Risk Summary

Available data from reports of pregnancy in clinical trials with ZYMFENTRA are insufficient to identify a drug associated risk of major birth defects, miscarriage or other adverse maternal or fetal outcomes. There are risks to the mother and the fetus associated with inflammatory bowel disease
in pregnancy (see Clinical Considerations).

Available observational data in pregnant women exposed to infliximab products administered intravenously showed no increased risk of major malformations among live births as compared to those exposed to non-biologics. Most TNF blockers, such as infliximab products, administered
intravenously are transferred across the placenta during the third trimester of pregnancy and may affect immune response in the in utero exposed infant. Infants exposed in utero should not be administered live vaccines for at least 6 months after birth (see Clinical Considerations). Because infliximab products do not cross-react with TNFα in species other than humans and chimpanzees, animal reproduction studies have not been conducted with ZYMFENTRA.

The background risk of major birth defects and miscarriage for the indicated populations is unknown. All pregnancies have a background risk of birth defect, loss, or other adverse outcomes. In the U.S. general population, the estimated background risk of major birth defects and
miscarriage in clinically recognized pregnancies is 2 to 4% and 15 to 20%, respectively.

Clinical Consideration

Disease-Associated Maternal and/or Embryo/Fetal Risk

Published data suggest that there is an increased risk of adverse pregnancy outcomes in women with inflammatory bowel disease associated with increased disease activity. Adverse pregnancy outcomes include preterm delivery (before 37 weeks of gestation), low birth weight (less than 2.5
kg) and small for gestational age at birth.

Fetal/Neonatal Adverse Reactions

The risk of fetal/neonatal adverse reactions with in utero exposure to infliximab-dyyb administered subcutaneously is unknown. However, most TNF blockers, such as infliximab products, cross the placenta and have been detected in infant serum up to 6 months following birth. Consequently, infants exposed to infliximab products may be at increased risk of infection, including disseminated infection which can become fatal. At least a six-month waiting period following birth is recommended before the administration of live vaccines (e.g., BCG vaccine or other live vaccines, such as the rotavirus vaccine) to infants exposed to intravenous infliximab in utero [see Warnings and Precautions (5.12)].

Cases of agranulocytosis in infants exposed to intravenous infliximab in utero have also been reported. Therefore, ZYMFENTRA, administered during pregnancy may affect immune responses in the in utero-exposed newborn and infant [see Adverse Reactions 6.2].

Data

Animal Data

Because infliximab products do not cross-react with TNFα in species other than humans and chimpanzees, animal reproduction studies have not been conducted with ZYMFENTRA.

8.2 Lactation

Risk Summary

There are no data on the presence of infliximab-dyyb or its metabolites in either human or animal milk, the effects on the breastfed infant, or the effects on milk production after subcutaneous administration. Published literature show that infliximab is present at low levels in human milk after intravenous administration. Systemic exposure in a breastfed infant is expected to be low because infliximab products are largely degraded in the gastrointestinal tract. The developmental and health benefits of breastfeeding should be considered along with the mother’s clinical need for ZYMFNETRA and any potential adverse effects on the brestfed child from ZYMFENTRA or from the underlying maternal condition.

8.4 Pediatric Use

The safety and effectiveness in pediatric patients have not been established.

8.5 Geriatirc Use

Clinical trials of ZYMFENTRA did not include sufficient numbers of sugjects aged 65 and over (8 subjects with UC and 6 subjects with CD) to determined whether they respond differently from younger subjects.

11 DESCRIPTION

Infliximab-dyyb, a tumor necrosis factor (TNF) blocker, is a chimeric IgG1κ monoclonal antibody (composed of human constant and murine variable regions). It has a molecular weight of approximately 145.9 kDa. Infliximab-dyyb is produced by a recombinant murine myeloma cell line, SP2/0.

ZYMFENTRA (inifliximab-dyyb) injection for subcutaneous use is a sterile, preservative-free, clear to opalescent, colorless to pale brown solution.

ZYMFENTRA is supplied in a single-dose prefilled syringe with 29 gauge fixed 1/2 inch needle, prefilled syringe with 29 gauge fixed 1/2 inch needle with needle guard, or prefilled pen with 27 gauge fixed 1/2 inch needle.

Each mL of solution contains 120 mg infliximab-dyyb, acetic acid (0.19 mg), polysorbate 80 (0.5 mg), sodium acetate (0.56 mg), sorbitol (45 mg) and Water for Injection, USP. The pH is 5.0.

12 CLINICAL PHAMACOLOGY

12.1 Mechanism of Action

Infliximab-dyyb neutralize the biological activity of TNFα by binding with high affinity to the soluble and transmembrane forms of TNFα and inhibit binding of TNFα with its receptors. Infliximab-dyyb has shown biological activities, such as TNFα neutralization activity and TNFα binding affinities, complement 1q (C1q) binding affinity and crystallizable fragment (Fc) receptor binding affinities in a wide variety of in vitro bioasays. The relationship of these biological response markers to the mechanism(s) by which infliximab-dyyb exerts its clinical effects is unknown.

12.2 Pharmacodynamics

No formal pharmacodynamic studies have been conducted.

12.3 Phamacokinetics

Following single and multiple subcutaneous dosing of infliximab-dyyb, exposures to infliximab-dyyb (i.e., AUC) are proportionally increased over the dose range from 120 mg to 240 mg (2 times the recommended dosage). After a single subcutaneous dose of infliximab-dyyb 120 mg in healthy subjects, the median (SD) Cmax and AUCinf were 10.0 (3.2) mcg/mL and 6945.6 (2830.2) mcg·h/mL, respectively. Following recommended subcutaneous maintenance dose of ZYMFENTRA (120 mg every 2 weeks) in adult subjects with UC and CD from Week 10 after intravenous induction treatment with infliximab-dyyb, steady-state was achieved by Week 22, and the mean (SD) trough serum concentrations of infliximab-dyyb at steady-state were 14.6 (7.8) mcg/mL and 14.6 (8.9) mcg/mL in subjects with UC and CD, respectively. Pharmacokinetics are comparable between healthy subjects, and subjects with UC or CD.

Absorption

In healthy subjects, the median time to reach the maximum serum concentration (Tmax) was 7 days after a single subcutaneous dose of infliximab-dyyb 120 mg. In healthy subjects, AUCinf following a single subcutaneous dosed of infliximab-dyyb 120 mg was approximately 23% relative to a single intravenous dose of infliximab-dyyb 5 mg/kg. Following infliximab-dyyb 120 mg subcuaneosly every 2 weeks, steady state AUC for 8-week internal was 25-35% higher compared to infliximab-dyyb 5 mg/kg administered intravenously every 8 weeks in subjects with UC and CD.

Distribution

Population pharmacokinetic analyses showed that the volume of distribution of infliximab-dyyb was 3.36L.

Elimination

In healthy subjects, the mean half-life was 332 hours after a single subcutaneous dose of infliximab-dyyb 120 mg.

Populatoin pharmacokinetic analyses showed that the clearance of infliximab-dyyb was 0.013 L/hr and the clearance was increased in the presence of anti-drug antibody.

The metabolic pathway of infliximab has not been characterized. As a IgG1κ monoclonal antibody, infliximab is expected to be degraded into small peptides and amino acids via catabolic pathways in the same manner as endogenous IgG.

Specific Populations

Weight

Population pharmacokinetic analysis indicated that exposure to infliximab-dyyb was inversely related to body weight. However, the magnitude of body weight effect on systemic exposure was not clinically meaningful in adult subjects with UC and CD weighing from 39 to 130 kg.

Age, Sex and Race

Age (≥65 years ofld), sex, or race did not have a clinically meaningful effect on pharmacokinetics of infliximab-dyyb.

Drug Interaction Studies

Population pharmacokinetic analysis showed that co-administered methotrexate did not have clinically meaningful effect on the pharmacokinetics of infliximab-dyyb.

12.6 Immunogenicity

The observed incidence of anti-drug antibodies is highly dependent on the sensitivity and specificity of the assay. Difference in assay methods preclude meaningful comparisons of the incidence of anti-drug antibodies in the studies described below with the incidence of anti-drug antibodies in other studies, including those of infliximab-dyyb or of other infliximab products.

In UC and CD clinical studies (UC Trial I and CD Trial I), approximately 64% subjects developed anti-drug antibodies to infliximab-dyyb following induction treatment with infliximab-dyyb intravenously and maintenance treatment with ZYMFENTRA by Week 54 [183/287 (64%) in subjects with UC, and 151/232 (65%) in subjects with CD] [see Clinical Studies (14)]. Among subjects with anti-drug antibodies, 92% had neutralizing antibodies [161/183 (88%) subjects with UC, and 147/151 (97%) subjects with CD]. Use of concomitant immunosuppressant agents (azathioprine, 6-mercaptopurine and methotrexate) appeared to reduce the frequency of ADA to infliximab-dyyb.

Anti-Drug Antibody Effects on Pharmacokinetics

Subjects who were positive for anti-drug antibodies showed lower infliximab-dyyb trough seum concentrations of infliximab-dyyb by approximately 30 to 40% compared to subjects who were negative for anti-drug antibodies. In some subjects with high titers of anti-drug antibodies and positive neutralizing antibodies, trough seum concentrations of infliximab-dyyb were below the lower limit of quantitation (<0.1 mcg/mL). There was no identified clinically significant effect of anti-drug antibodies on the safety and effectiveness of ZYMFENTRA in Study UC I and Study CD I.

13 NONCLINICAL TOXICOLOGY

13.1 Carcinogenesis, Mutagenesis, Impairment of Fertility

Long-term animal studies of infliximab-dyyb have not been conducted to evaluate the carcinogenic potential or its effect on fertility.

14 CLINICAL STUDIES

14.1 Adult Ulcerative Colitis

The safety and efficacy of ZYMFENTRA were assessed in a randomized, double-blind, placebo-controlled clinical trial (UC Trial I; NCT04205643) in adult subjects with moderately to severely active UC (defined as a modified Mayo score [mMS] between 5 to 9 with an endoscopic subscore [ES] of 2 or 3). The mMS is a 3-component Mayo score (0-9), which consists of following subscores (0 to 3 for each subscore): stool frequency (SFS), rectal bleeding (RBS), and findings on centrally read endoscopy score (ES). An ES of 2 was defined by marked erythema, lack of vascular pattern, any friability, and/or erosions, and a score of 3 was defined by spontaneous bleeding and ulceration.

Subjects had demonstrated an inadequate response or intolerance to treatment with corticosteroids alone or in combination with 6-mercaptopurine or azathioprine. Subjects were permitted to use stable doses of oral aminosalicylates, oral corticosteroids (prednisone ≤20 mg/day or equivalent, budesonide ≤9 mg/day), UC-related antibiotics, and/or immunomodulatory agents (azathioprine, 6-mercaptopurine, or methotrexate). Corticosteroid tapering was permitted after Week 10.

All subjects received three intravenous induction doses of 5 mg/kg of infliximab-dyyb at Weeks 0, 2 and 6. In order to be randomized to treatment in UC Trial I, subjects had to be in clinical response at Week 10. Clinical response was defined as a decrease from baseline in the mMS of at least 2 points and at least 30%, with an accompanying decrease in the RBS of at least 1 point or an aabsolute RBS of 0 or 1 point.

A total of 438 subjects were randomized at Week 10 in a double-blind fashion (2:1) to ZYMFENTRA 120 mg as a subcutaneous injection or placebo every two weeks.

At the time of randomization into the double-blind phase (Week 10), 92% were receiving aminosalicylates, 41% were receiving oral corticosteroids, and 22% were receiving immunomodulators including AZA, 6-MP or MTX.

A total of 10% of randomized subjects had prior exposure to biological poucts or JAK inhibitors.

Subjects in the boule-blind phase had a mean age of 39 years (range 18 to 75 years); 44% were female; and 98% identified as White, and 2% as American Indian or Alaska Native.

The primary endpoint was the proportion of subjects in clinical remission at Week 54. Wecondary endpoints included the proportion of subjects achieving histologic-endoscopic mucosal improvement and corticosteroid-fee remission at Week 54 (see Table 3).

Table 3: Proportion of Subjects with Ulcerative Colitis Meeting Effficacy Endpoints at Week 54 in UC Trial I
Endpoint |  | ZYMFENTRA | Placebo | Treatment Differencea; and 95% CI
Clinical Remissionb at Week 54
Total population |  | N=294; 43% | N=144; 21% | 21%; (12, 29)
No prior biological product/JAK inhibitor exposure |  | N=265; 45% | N=131; 21%
Prior biological product/JAK inhibitor exposure |  | N=29; 31% | N=13; 15%
Histologic-Endoscopic Mucosal Improvementd at Week 54
Total population |  | N=294; 36% | N=144; 17% | 18%; (9, 26)
No prior biological product/JAK inhibitor exposure |  | N=265; 36% | N=131; 18%
Prior biological product/JAK inhibitor exposure |  | N=29; 31% | N=13; 8%
Corticosteroid-Fee Remissione at Week 54
Total population |  | N=120; 37% | N=61; 18% | 17%f; (3, 29)
No prior biological product/JAK inhibitor |  | N=107; 36% | N=56; 18%
Prior biological product/JAK inhibitor exposure |  | N=13; 39% | N=5; 20%
CI = confience interval, JAK = Janus kinase
a Treatement difference (adjusted for stratification factors of previous exposure to biological product and/or JAK inhibitor, use of treatment with oral corticosteoids Week 0, and clinical remission status at Week 10.)
b Clinical remissio is defined using the mMS as SFS of 0 or 1 point; RBS of 0 point; and ES of 0 or 1 point (excluding friability).
c p < 0.0001
d Histologic-endoscopic mucosal improvement is defined as an absolute ES of 0 or 1 point (excluding friability) from mMS and an absoluted Robarts Histopathology Index (RHI) score of ≤3 poitns with no lamina propria neutrophils, no neutrophils in epithelium, no erosion or ulceration.
e Corticosteroid-free remission is defined as being in clinical remission by mMS in addition to not requiring any treatment with corticosteroid for at least 8 weeks at Week 54, among the patients who used oral cotricosteroids at baseline.
f p < 0.05

The relationship between histologic-endoscopic mucosal improvement at Week 54 and diasease progression and longer-term outcomes after Week 54 was not evaluated in UC Trial I.

14.2 Adult Crohn's Disease

The safety and efficacy of ZYMFENTRA were assessed in a randomized, double-blind, placebo-controlled clinical studies (CD Trial I; NCT03945019) in adult subjects with moderately to severely active CD, defined as Crohn's Disease Activity Index (CDAI) score of 220 to 450 points, and a centrally-reveiwed Simplified Endoscopic Activity Score for Crohn’s Disease (SES-CD) of ≥6 points for ileal-colonic CD (or ≥4 points for isolated ileal disease).

Subjects had demonstrated an inadequate response or intolerance to treatment with corticosteroids and/or immunosuppressants. Subjects were permitted to use stable doses of oral amisosalicylates, oral corticosteroids (prednisone ≤20 mg/day or equivalent, budesonide ≤9 mg/day), CD-related antibiotics and/or immunomodulatory agents (azathioprine, 6-mercaptopurine, or methotrexate). Corticosteroid dose was tapered after Week 10.

All subjects received three intravenous induction doses of 5 mg/kg infliximab-dyyb at Week 0, 2 and 6. In order to be ranomized to treatment in CD Trial I, subjects had to be in clinical response at Week 10. Clinical response was defined as a decrease from baseline in CDAI of at least 100 points (i.e., CDAI-100 responders).

A total of 323 subjects were randomized at Week 10 in a double-blind fashion (2:1) to ZYMFENTRA 120 mg as a subcutaneous injection or placebo every 2 weeks.

At the time of randomization into thd double-blind phase (Week 10), 61% were receiving aminosalicylates, 40 % were receiving oral corticosteroids, and 32% were receiving immunomodulators including azathioprine, 6-mercaptopurine, or methotrexate.

A total of 11% of randomized subjects had prior exposure to biological products.

Subjects in the double-blind phase had a mean age of 35 years (range 18 to 75 years); 40% were female; and 91% identified as White, 4% identified as American Indian or Alaska Native, 4% identified as Asian, 0.3% as Black or African American, and 1% identified as another racial group.

The co-primary endopoints were clinical remission (based on CDAI) and endoscopic response at Week 54. Secondary endpoints included endoscopic remission, and corticosteroid-free remission at Week 54 (see Table 4).

Table 4: Proportion of Subjects with Crohn's Disease Meeting Efficacy Endpoints at Week 54 in CD Trial I
Endpoint | ZYMFENTRA | Placebo | Treatment Differencea; and 95% CI
Clinical Remission (Based on CDAI)bat Week 54
Total population | N=216; 63% | N=107; 30% | 35%c; (24, 45)
No prior biological product expousre | N=191; 62% | N=98; 31%
Prior biological product exposure | N=25; 72% | N=9; 22%
Endoscopic responsed at Week 54
Total population | N=216; 50% | N=107; 87% | 34%c; (23, 43)
No prior biological product exposure | N=191; 51% | N=98; 17%
Prior biological product exposure | N=25; 48% | N=9; 22%
Enoscopic Remissione at Week 54
Total population | N=216; 35% | N=107; 10% | 25%c; (16, 33)
No prior biological product exposure | N=191; 35% | N=98; 10%
Prior biological product exposure | N=25; 36% | N=9; 11%
Corticosteroid-free Remissionf at Week 54
Total population | N=92; 40% | N=43; 21% | 19%g
No prior biological product expousre | N=81; 35% | N=40; 23%
Prior biological product exposure | N=11; 82% | N=3; 0%
CI=confidence internal, CDAI=Crohn's Disease Activity Index, JAK=Janus kinase
a Treatment difference (adjusted for stratification factors of previous exposure to biological product, use of treatment with oral corticosteroids at Week 0, and clinical remission status at Week 10).
b Clinical remission (based on CDAI) is defined as an absolute CDAI score of <150 points.
c p < 0.0001.
d Endoscopic response is defined as a >50% decrease in SES-CD from the baseline value.
e Endoscopic remission is defined as an absolute SES-CD score of ≤4 with no sub-score of >1.
f Corticosteroid-free remission is defined as being in clinical remission in additio to not receiving any corticosteroid for at least 8 weeks prior to Week 54, among the subjects who used oral corticosteroids at baseline.
g p < 0.05

16 HOW SUPPLIED/STORAGE AND HANDLING

How Supplied

ZYMFENTRA (Infliximab-dyyb) injection for subcutaneous use is supplied as a sterile, preservative-free, clear to opalescent, colorless to pale brown solution in a single-use prefilled syringe, prefilled syringe with needle guard or prefilled pen. The syringe is fitted with a needle shield which are not made with natural rubber latex or any derivatives from natural rubber latex in any ingredient.

Prefilled Syringe

Each prefilled syringe is equipped with a 29 gauge fixed 1/2 inch needle with a rigid needle shield and a plunger stopper. The following configurations are available:

- One prefilled syringe (120 mg/mL solution) and one dose tray with two alcohol pads. (NDC: 72606-025-05)
- Two prefilled syringes (120 mg/mL solution) and two dose trays with two alcohol pads. (NDC: 72606-025-06)
- Four prefilled syringes (120 mg/mL solution) and four dose trays with four alcohol pads. (NDC: 72606-025-07)
- Six prefilled syringes (120 mg/mL solution) and six dose trays with six alcohol pads. (NDC: 72606-025-08)

Prefilled Syringe with Needle Guard

Each prefilled syringe is equipped with a 29 gauge fixed 1/2 inch needle with a rigid needle shield and an automatic needle guard, and a plunger stopper. The following configurations are available:

- One prefilled syringe with needle guard (120 mg/mL solution) and one does tray with two alcohol pads. (NDC: 72606-025-09)
- Two prefilled syringes with needle guard (120 mg/mL solution) and two dose trays with two alcohol pads. (NDC: 72606-025-10)
- Four prefilled syringes with needle guard (120 mg/mL solution) and four dose trays with four alcohol pads. (NDC: 72606-025-11)
- Six prefilled syringes with needle guard (120 mg/mL solution) and six dose trays with six alcohol pads. (NDC: 72606-025-12)

Prefilled Pen

Each prefilled pen is equipped with a 27 gauge fixed 1/2 inch needle with a rigid needle shield and a plunger stopper. The following configurations are available:

- One prefilled pen (120 mg/mL solution) and one dose tray with two alcohol pads. (NDC: 72606-025-01)
- Two prefilled pens (120 mg/mL solution and two dose trays with two alcohol pads. (NDC: 72606-025-02)
- Four prefilled pens (120 mg/mL solution) and four dose trays with four alcohol pads. (NDC: 72606-025-03)
- Six prefilled pens (120 mg/mL solution) and six dose trays with six alcohol pads. (NDC: 72606-025-04)

Storage and Handling

Store in refrigerator at 2°C to 8°C (36°F to 46°F). DO NOT FREEZE. Keep the product in its outer carton until time of administration in order to protect from light.

If needed, the product may be stored at room temperature at 20°C to 25°C (68°F to 77°F) for up to 14 days with protection from light. Once the product has been stored at room temperature, it should not be placed back into the refrigerator. The product must be discarded if not used within the 14 days.

17 PATIENT COUNSELING INFORMATION

Advise the patient or thier caregiver to read the FDA-Approved Patient Labeling (Medication Guide and Instructions for Use).

Patients or their caregivers should be advised of the potential benefits and risks of ZYMFENTRA. Healthcare providers should instruct their patients or their caregivers to read the Medication Guide before starting ZYMFENTRA therapy and to reread it each time they receive an injection.

Infections

Inform patients that ZYMFENTRA increases the risk for developing serious infections. Instruct patients of the importance of contacting their healthcare provider if they develop any symptoms of an infection, including tuberculosis, invasive fungal infections, and reactivation of hepatitis B virus infections [see Warnings and Precautions (5.1, 5.3)].

Malignancies

Malignancies have been reported among children, adolescents and young adults who received treatment with TNF blockers. Patients should be counseled about the risk of lymphoma and other malignancies while receiving ZYMFENTRA [see Warnings and Precautions (5.2)].

Hepatotoxicity

Instruct patients to seek medical attention if they develop signs or symptoms of hepatotoxicity (e.g., jaundice) [see Warnings and Precautions (5.4)].

Congestive Heart Failure

Instruct patients to seek medical attention and consult their prescriber if they develop signs or symptoms of heart failure [see Warnings and Precautions (5.5)].

Hematologic Reactions

Instruct patients to seek immediate medical attention if they develop signs and symptoms suggestive of blood dyscrasias or infection (e.g., persistent fever) while on ZYMFENTRA [see Warnings and Precautions (5.6)].

Hypersensitivity

Advise patients to seek immediate medical attention if they experience any symptoms of serious hypersensitivity reactions [see Warnings and Precautions (5.7)].

Neurologic Reactions

Advise patients to seek medical attention if they develop signs or symptoms of neurologic reactions [see Warnings and Precautions (5.8)].

Live Vaccines/Therapeutic Infectious Agents

Instruct ZYMFENTRA-treated patients to avoid receiving live vaccines or therapeutic infectious agents [see Warnings and Precautions (5.12)]

Administration

Instruct patients to follow sharp disposal recommendations, as described in the Instructions for Use.

Manufactured by:
CELLTRION, Inc.
23, Academy-ro,
Yeonsu-gu, Incheon
22014, Republic of Korea
U.S. License No. 1996

Distributed by:
CELLTRION USA, Inc.
One Evertrust Plaza Suite 1207,
Jersey City, New Jersey,
07302, USA
CELLTRION USA, Inc.

© CELLTRION, Inc.

MEDICATION GUIDE
ZYMFENTRATM (Zim fen' trah)
(infliximab-dyyb)
injection, for subcutaneous use

Read the Medication Guide that comes with ZYMFENTRA before you receive the first treatment, and before each time you receive a treatment of ZYMFENTRA. This Medication Guide does not take the place of talking with your doctor about your medical condition or treatment.

What is the most important information I should know about ZYMFENTRA?

ZYMFENTRA may cause serious side effects, including:
1. Risk of infection
ZYMFENTRA is a medicine that affects your immune system. ZYMFENTRA can lower the ability of your immune system to fight infections. Serious infections have happened in patients receiving ZYMFENTRA. These infections include tuberculosis (TB) and infections caused by viruses, fungi, or bacteria that have spread throughout the body. Some patients have died from these infections.

- Your doctor should test you for TB before starting ZYMFENTRA.
- Your doctor should monitor you closely for signs and symptoms of TB during treatment with ZYMFENTRA.

Before starting ZYMFENTRA, tell your doctor if you:

- think you have an infection. You should not start receiving ZYMFENTRA if you have any kind of infection.
- are being treated for an infection.
- have signs of an infection, such as a fever, cough, flu-like symptoms.
- have any open cuts or sores on your body.
- get a lot of infections or have infections that keep coming back.
- have diabetes or an immune system problem as people with these conditions have a higher chance for getting infections.
- have TB, or have been in close contact with someone with TB.
- live or have lived in certain parts of the country (such as the Ohio and Mississippi River valleys) where there is an increased risk for getting certain kinds of fungal infections (histoplasmosis, coccidioidomycosis, or blastomycosis); these infections may develop or become more severe if you receive ZYMFENTRA. If you do not know if you have lived in an area where histoplasmosis, coccidioidomycosis, or blastomycosis is common, ask your doctor.
- have or have had hepatitis B.
- use the medicines KINERET (anakinra), ORENCIA (abatacept), or other medicines called biologics used to treat the same conditions as ZYMFENTRA.

After starting ZYMFENTRA, if you have an infection, any sign of an infection including a fever, cough, flu-like symptoms, or have open cuts or sores on your body, call your doctor right away. ZYMFENTRA can make you more likely to get infections or make any infection that you have worse.

2. Risk of Cancer

- There have been cases of unusual cancers in children and teenage patients using tumor necrosis factor (TNF) blocker medicines, such as ZYMFENTRA.
- For people receiving TNF blocker medicines, including ZYMFENTRA, the chances of getting lymphoma or other cancers may increase.
- Some people receiving TNF blockers, including ZYMFENTRA, developed a rare type of cancer called hepatosplenic T-cell lymphoma. This type of cancer often results in death. Most of these people were male teenagers or young men. Also, most people were being treated for Crohn's disease or ulcerative colitis with a TNF blocker and another medicine called azathioprine or 6-mercaptopurine.
- People who have been treated for Crohn's disease and ulcerative colitis, for a long time may be more likely to develop lymphoma. This is especially true for people with very active disease.
- Some people treated with infliximab products, such as ZYMFENTRA, have developed certain kinds of skin cancer. If any changes in the appearance of your skin or growths on your skin occur during or after your treatment with ZYMFENTRA, tell your doctor.
- Patients with Chronic Obstructive Pulmonary Disease (COPD), a specific type of lung disease, may have an increased risk for getting cancer while being treated with ZYMFENTRA.
- Tell your doctor if you have ever had any type of cancer. Discuss with your doctor any need to adjust medicines you may be taking.

See the section "What are the possible side effects of ZYMFENTRA?" below for more information.

What is ZYMFENTRA?
ZYMFENTRA is a prescription medicine used as an injection uner the skin (subcutaneous injection) by adults for the maintenance treatment of:

- moderately to severely active ulcerative colitis following treatment with an infliximab product given by intravenous infusion (IV).
- moderately to severely active Crohn's disease following treatment with an infliximab product given by intravenous infusion (IV).

It is not known if ZYMFENTRA is safe and effective in children under 18 years of age.

Do not take ZYMFNETRA if you:

- have had an allergic reaction to ZYMFENTRA, other infliximab products, any murine proteins or any of the ingredients in ZYMFENTRA. See the end of this Medication Guide for a complete list of ingredients in ZYMFENTRA.

Before you receive ZYMFENTRA, tell your doctor all of your medical conditions, including if you:

- have an infection (see "What is the most important information I should know about ZYMFENTRA?").
- have other liver problems including liver failure.
- have heart failure or other heart conditions. If you have heart failure, it may get worse while you receive ZYMFENTRA.
- have or have had any type of cancer.
- have COPD (Chronic Obstructive Pulmonary Disease), a specific type of lung disease. Patients with COPD may have an increased risk of getting cancer while receiving ZYMFENTRA.
- have or have had a condition that affects your nervous system such as:
  - multiple sclerosis, or Guillain-Barré syndrome, or
  - if you experience any numbness or tingling, or
  - if you have had a seizure.

- have recently received or are scheduled to receive a vaccine. Adults receiving ZYMFENTRA should not receive live vaccines (for example, the Bacille Calmette-Guérin [BCG] vaccine) or treatment with a weakened bacteria (such as BCG for bladder cancer). Adults should have all of their vaccines brought up to date before starting treatment with ZYMFENTRA.
- are pregnant or plan to become pregnant, are breastfeeding or plan to breastfeed. You and your doctor should decide if you should receive ZYMFENTRA while you are pregnant or breastfeeding.

If you have a baby and you were receiving ZYMFENTRA during your pregnancy, it is important to tell your baby's doctor and other healthcare professionals about your ZYMFENTRA use so they can decide when your baby should receive any vaccine. Certain vaccinations can cause infections.

If you received ZYMFENTRA while you were pregnant, your baby may be at higher risk for getting an infection. If your baby receives a live vaccine within 6 months after birth, your baby may develop infections with serious complications that can lead to death. This includes live vaccines such as the BCG, rotavirus, or any other live vaccines. For other types of vaccines, talk with your doctor.

How should I receive ZYMFENTRA?

- Use ZYMFENTRA exactly as your doctor tells you to.

- ZYMFENTRA is provided as a single-dose prefilled syringe, single-dose prefilled syringe with needle guard or single-dose prefilled pen. Your healthcare provider will prescribe the type that is best for you.
- If your healthcare provider decides that you or your cargiver can give your injections of ZYMFENTRA at home, you or your caregiver should be shown the right way to prepare and inject ZYMFENTRA.
- Do not try to inject ZYMFENTRA yourself until you or your caregiver have been shown how to inject ZYMFENTRA by your healthcare provider.
- ZYMFENTRA is injected under your skin (subcutaneously) 1 time every two weeks.
- Inject ZYMFENTRA under the skin (subcutaneous injection), in your upper arms, stomach area (abdomen), or upper legs (thighs).
- Do no give an injection in an area of the skin that is tender, bruised, red or hard.
- Use a different injection site each time you use ZYMFENTRA.
- If you are not able to inject ZYMFENTRA at your regular scheduled time or you miss a dose of ZYMFENTRA, inject the dose as soon as possible. Then, inject your next dose every two weeks thereafter. If you are not sure when to inject ZYMFENTRA, call your healthcare provider.
- If you inject more than prescribed, call your doctor right away.
- Be sure to keep all of your scheduled follow-up appointments.

Read the detailed Instructions for Use at the end of this Medication Guide for insructions about how to prepare and inject a dose of ZYMFENTRA, and how to properly throw away (dispose of) used needles and syringes. The syringe and needle must never be re-used. After the rubber stopper is puntured, ZYMFENTRA can become contaiminated by harmful bacteria which could cause an infection if re-used. Therefore, throw away any unused portion of ZYMFENTRA.

What should I avoid while taking ZYMFENTRA?
Do not take ZYMFENTRA together with other medicines medicines called biologics that are used to treat the same conditions as ZYMFENTRA.

Tell your doctor about all the medicines you take, including prescription and over-the-counter medicines, vitamins, and herbal supplements. These include any other medicines to treat Crohn's disease, or ulcerative colitis.

Know the medicines you take. Keep a list of your medicines and show them to your doctor and pharmacist when you get a new medicine.

What are the possible side effects of ZYMFENTRA?
ZYMFENTRA can cause serious side effects, including (see "What is the most important information I should know about ZYMFENTRA?"):
Serious Infections

- Some patients, especially those 65 years and older have had serious infections while receiving infliximab products, such as ZYMFENTRA. These serious infections include TB and infections caused by viruses, fungi, or bacteria that have spread throughout the body or cause infections in certain areas (such as skin). Some patients die from these infections. If you get an infection while receiving treatment with ZYMFENTRA your doctor will treat your infection and may need to stop your ZYMFENTRA treatment.
- Tell your doctor right away if you have any of the following signs of an infection while receiving or after receiving ZYMFENTRA:

- a fever
- feel very tired
- have a cough

- have flu-like symptoms
- warm, red, or painful skin

- Your doctor will examine you for TB and perform a test to see if you have TB. If your doctor feels that you are at risk for TB, you may be treated with medicine for TB before you begin treatment with ZYMFENTRA and during treatment with ZYMFENTRA.
- Even if your TB test is negative, your doctor should carefully monitor you for TB infections while you are receiving ZYMFENTRA. Patients who had a negative TB skin test before receiving infliximab products may develop active TB after receiving infliximab products.
- If you are a chronic carrier of the hepatitis B virus, the virus can become active while you are being treated with ZYMFENTRA. In some cases, patients have died as a result of hepatitis B virus being reactivated. Your doctor should do a blood test for hepatitis B virus before you start treatment with ZYMFENTRA, while you are being treated and for several months after you finish treatment. Tell your doctor if you have any of the following symptoms:

- feel unwell
- poor appetite

- tiredness (fatigue)
- fever, skin rash, or joint pain

Liver Injury

Some patients receiving infliximab products have developed serious liver problems. Tell your doctor if you have:

- jaundice (skin and eyes turning yellow)
- dark, brwon-colored urine
- pain on the right side of your stomach area (right-sided abdominal pain)

- fever
- extreme tiredness (sevre fatigue)

Heart Failure

If you have a heart problem called congestive heart failure, your doctor should check you closely while you are receiving ZYMFENTRA. Your congestive heart failure may get worse while you are receiving ZYMFENTRA. Be sure to tell your doctor of any new or worse symptoms including:

- shortness of breath
- swelling of ankles or feet

- sudden weight gain

Treatment with ZYMFENTRA may need to be stopped if you get new or worse congestive heart failure.

Blood Probelms

In some patiens receiving infliximab products, the body may not make enough of the blood cells tha help fight infections or help stop bleeding. Tell your doctor if you:

- have a fever that does not go away
- bruise or bleed very easily

- look very pale

Allergic Reactions
Some patients have had allergic reactions to infliximab products. Some of these reactions were severe. These reactions can happen while you are getting your ZYMFENTRA treatment or shortly afterward. Your doctor may need to stop or pause your treatment with ZYMFENTRA and may give you medicines to treat the allergic reaction. Signs of an allergic reactio can include:

- hives (red, raised, itchy patches of skin)
- difficulty breathing
- chest pain

- high or low blood pressure
- fever
- chills

Some patients treated with infliximab products have had delayed allergic reactions. Tell your doctor right away if you have any of these signs of delayed reaction to ZYMFENTRA:

- fever
- rash
- headache
- sore throat

- muscle or joint pain
- swelling of the face and hands
- difficulty swallowing

Nervous System Disorders

Some patients receiving infliximab products have developed problems with their nervous system. Tell your doctor if you have:

- changes in your vision
- numbness or tingling in any part of your body

- seizures
- weakness in your arms or legs

Some patients have experienced a stroke within approximately 24 hours of their infusion with infliximab products. Tell your doctor right away if you have symptoms of a stroke which may include: numbness or weakness of the face, arm, or leg, especially on one side of the body; sudden confusion, trouble speaking or understanding; sudden trouble seeing in one or both eyes, sudden trouble walking, dizziness, loss of balance or coordination or a sudden, severe headache.

Lupus-like Syndrome

Some patient have developed symptoms that are like the symptoms of Lupus. If you develop any of the following symptoms, your doctor may decide to stop your treatment with ZYMFENTRA:

- chest disomfort or painthat does not go away
- shortness of breath

- joint pain
- rash on the cheeks or arms that gets worse in the sun

The most common side effects of ZYMFENTRA include:

- COVID-19
- respiratory infections, such as sinus infections and sore throat
- injection site reactions
- headache
- abdominal pain
- abnormal liver enzymes

- joint pain
- diarrhea
- high blood pressure
- urinary tract infections
- dizziness

Tell your doctor about any side effect that bothers you or does not go away.

These are not all of the side effects with ZYMFENTRA. Ask your doctor or pharmacist for more information.
Call your doctor for medical advice about side effects. You may report side effects to FDA at 1-800-FDA-1088.

How should I store ZYMFENTRA?

- Store ZYMFENTRA prefilled syringes and prefilled pens in a refrigerator between 36°F to 46°F (2°C to 8°C).
- If needed, ZYMFENTRA prefilled syringes and prefilled pens may be stored at room temperature between 68°F to 77°F (20°C to 25°C) for up to 14 days with protection from light.
- When ZYMFENTRA prefilled syringes and prefilled pens have reached room temperature, do not put ZYMFENTRA back in the refrigerator. ZYMFENTRA must be thrown away (discarded) if not used within the 14 days.
- Do not freeze ZYMFENTRA.
- Do not shake ZYMFENTRA.
- Keep ZYMFENTRA in the original carton until ready to use to protect it from light.

General information about ZYMFENTRA
Medicines are sometimes prescribed for purposes other than those listed in a Medication Guide.

You can ask your doctor or pharmacist for information about ZYMFENTRA that is written for health professionals.

Do not use ZYMFENTRA for a condition for which it was not prescribed. Do not give ZYMFENTRA to other people, even if they have the same symptoms that you have.

For more information call 1-888-804-3433.

What are the ingredients in ZYMFENTRA?
The active ingredient is infliximab-dyyb.

The inactive ingredients in ZYMFENTRA include: acetic acid, polysorbate 80, sodium acetate, and sorbitol in water for injections. No preservatives are present.

Manufactured by: CELLTRION, Inc. 23, Academy-ro, Yeonsu-gu, Incheon, 22014, Republic of Korea
U.S. License No. 1996 ©CELLTRION, Inc.
Distributed by CELLTRION USA, Inc. One Evertrust Plaza Suite 1207, Jersey City, New Jersey, 07302, USA
For more information call 1-888-804-3433

This Medication Guide has been approved by the U.S. Food and Drug Administration Revised: 02/2024

INSTRUCTIONS FOR USE ZYMFENTRA (Zim fen' trah) (infliximab-dyyb) Injection for subcutaneous use only Single-Dose Prefilled Pen 120 mg/mL Rx Only

Read and follow the Instruction for Use that come with your ZYMFENTRA Prefilled Pen before you start using it and each time you get a refill. There may be new information. This information does not take the place of talking to your healthcare provider about your medical condition or treatment.

Figure A: Parts of ZYMFENTRA Prefilled Pen

Important Information

- Use the Prefilled Pen only if your healthcare provider has trained you on the right way to prepare for and to give an injection.
- Ask your healthcare provider how often you will need to give an injection.
- Rotate the injection site each time you give an injection. Each new injection site should be at least 1.2 inches away from the previous injection site.
- Do not shake the Prefilled Pen at any time.
- Do not remove the Cap until you are ready to inject.
- Do not share the Prefilled Pen with anyone.

How to store the Prefilled Pen

- Store the Prefilled Pen in a refrigerator between 36°F to 46°F (2°C to 8°C).
- Keep the Prefilled Pen in the original carton until use to protect it from light.
- Do not use the Prefilled Pen that has been left in direct sunlight.
- Do not freeze the Prefilled Pen. If the Prefilled Pen has been frozen, do not use the Prefilled Pen even if it is thawed.
- Do not warm the Prefilled Pen using heat sources such as hot water or a microwave. Let the Prefilled Pen naturally warm at room temperature between 68°F to 77°F (20°C to 25°C) for 30 minutes before giving an injection.
- When the Prefilled Pen has reached room temperature, do not put it back in the refrigerator. The Prefilled Pen must be thrown away (discarded) if not used within the 14 days.
- Keep the Prefilled Pen and all medicines out of the reach of children.

Prepare for the Injection

1. Gather the supplies for the injection.

1a. Prepare a clean, flat surface, such as a table or countertop, in a well-lit area.
1b. Remove 1 Prefilled Pen from the carton stored in your refrigerator.
Note: Return the carton with any unused Prefilled Pens to refrigerator immediately after taking out one Prefilled Pen.
1c. Make sure you have the following supplies:
- Prefilled Pen
- 1 Alcohol swab
Not included in the carton:
- 1 Cotton ball or gauze
- 1 Adhesive bandage
- FDA-cleared sharps disposal container

2. Inspect the Prefilled Pen.

2a. Make sure you have the correct medicine (ZYMFENTRA).

2b. Check the expiration (EXP) date on the label of the Prefilled Pen (See Figure B).

2c. Look at the Prefilled Pen and make sure it is not cracked or damaged.

- Do not use the Prefilled Pen if:
  - it is cracked or damaged.
  - the expiration (EXP) date has passed.

Figure B

3. Inspect the Medicine.

3a. Look through the Window and make sure that the liquid is clear, colorless to pale brown, and free of particles (see Figure C).

- Do not use the Prefilled Pen if the liquid is the discolored (yellow or dark brown), cloudy, or contains particles in it.
- You may see air bubbles in the liquid. This is normal.

Figure C

4. Wait 30 minutes.

4a. Leave the Prefilled Pen at room temperature 68°F to 77°F (20°C to 25°C) for 30 minutes to allow it to warm up (see Figure D).

- Do not warm the Prefilled Pen using heat sources such as hot water or a microwave.

Figure D

5. Choose an injection site (see Figure E).

5a. You may inject into:

- the front of your thighs.

- the stomach area (abdomen) except for the 2 inches around the belly button (navel).

- the outer area of the upper arm if you are a caregiver.

- Do not inject into skin that is within 2 inches of your belly button (navel), or is red, hard, tender, damaged, bruised, or scarred.
- Do not inject through your clothes.

5b. Rotate the injection site each time you give an injection.

- Do not inject the same injection site each time you give an injection.
- Each new injection site should be at least 1.2 inches away from the injection site you used before.

Figure E

6. Wash your han

6a. Wash your hands with soap and water and dry them thoroughly (see Figure F).

Figure F

7. Clean the injection site.

7a. Clean the injection site with an alcohol swab using a circular motion (see Figure G).
7b. Let the skin dry before injecting.

- Do not blow on or touch the injection site again before giving the injection.

Figure G

Give the injection

8. Remove the Cap.

8a. Hold the Prefilled Pen by the injector body with the Cap on top using one hand. Gently pull the Cap straight off with the other hand.

- Do not recap the Prefilled Pen.
- Do not remove the Cap until you are ready to inject.
- Do not touch the Needle or Needle Cover. Doing so may result in a needle stick injury.

8b. Dispose of the Cap in an FDA cleared sharps container (see Step 12 and Figure H).

Figure H

9. Place the Prefilled Pen on the injection site.

9a. Hold the Prefilled Pen so that you can see the Window.

9b. Without pinching or stretching the skin, place the Prefilled Pen over the injection site at a 90-degree angle (see Figure I).

Figure I

10. Give the injection (see Figure J).

10a. Press the Prefilled Pen firmly against the skin.

- When the injection starts you will hear the first loud "click" and the purple Plunger Rod will begin to fill the Window.

10b. Keep holding the Prefilled Pen firmly against the skin and listen for the second loud "click." This can take up to 10 seconds.

- Do not change the position of the Prefilled Pen after the injection has started.

10c. After you hear the second loud "click" continue to keep holding the Prefilled Pen firmly against the skin and count slowly to 5 to make sure you inject the full dose.

10d. Look at the Prefilled Pen and make sure that the purple Plunger Rod is filling the Window completely.

Figure J

11. Remove the Prefilled Pen from your skin.

11a. Remove the Prefilled Pen from your skin (see Figure K).

- After you remove the Prefilled Pen from the injection site, the needle will be automatically covered (see Figure L).
- If the Window has not turned completely purple or if the medicine is still injecting, this means you have not received a full dose. Call your healthcare provider immediately.
- You may see grey stopper in the Window. This is normal.
- Some bleeding may occur.
- Do not reuse the Prefilled Pen.
- Do not rub the injection site

Figure K

Figure L

After the injection

12. Throw away (dispose of) the Prefilled Pen.

12a. Put the used Prefilled Pen in an FDA-cleared sharps disposal container right away after use (see Figure M).

- Do not throw away (dispose of) the Prefilled Pen in your household trash.
  - If you do not have an FDA-cleared sharps disposal container, you may use a household container that is:
    - made of a heavy-duty plastic,
    - can be closed with a tight-fitting, puncture-resistant lid, without sharps being able to come out,
    - upright and stable during use,
    - leak-resistant, and
    - properly labeled to warn of hazardous waste inside the container.
  - When your sharps disposal container is almost full, you will need to follow your community guidelines for the right way to dispose of it. There may be state or local laws about how you should throw away used needles and syringes. For more information about safe sharps disposal, and for specific information about sharps disposal in the state that you live in, go to the FDA's website at: http://www.fda.gov/safesharpsdisposal.
  - Do not dispose of your used sharps disposal container in your household trash unless your community guidelines permit this. Do not recycle your used sharps disposal container.

Figure M

13. Care for the injection site.

13a. Treat the injection site by gently pressing, not rubbing, a cotton ball or gauze to the site and apply an adhesive bandage, if necessary.

Manufactured by: CELLTRION, Inc., 23, Academy-ro, Yeonsu-gu, Incheon, 22014, Republic of Korea
US License Number 1996

Distributed by: CELLTRION USA, Inc., 1 Evertrust Plaza Suite 1207, Jersey City, NJ 07302

INSTRUCTIONS FOR USE ZYMFENTRA (Zim fen' trah) (infliximab-dyyb) Injection for subcutaneous use only Single-Dose Prefilled Syringe 120 mg/mL Rx Only

For subcutaneous use only

Read and follow Instructions for Use that come with your ZYMFENTRA Prefilled Syringe before using it and each time you get a refill. There may be new information. This information does not take the place of talking to your healthcare provider about your medical condition or treatment.

Figure A: Parts of ZYMFENTRA Prefilled Syringe

Caution! Do not remove the Cap until you are ready to inject. When you remove the Cap, do not recap the Prefilled Syringe.

Important Information

- Use the Prefilled Syringe only if your healthcare provider has trained you on the right way to prepare for and to give an injection.
- Ask your healthcare provider how often you will need to give an injection.
- Rotate the injection site each time you give an injection. Each new injection site should be at least 1.2 inches away from the previous injection site.
- Do not use Prefilled Syringe if it has been dropped or is visibly damaged.
- Do not reuse the Prefilled Syringe.
- Do not shake the Prefilled Syringe at any time.
- Do not share the Prefilled Syringe with anyone.
- Do not pull back on the plunger rod at any time.
- Only use each Prefilled Syringe for one injection.

How to store the Prefilled Syringe

- Store the Prefilled Syringe in a refrigerator between 36°F to 46°F (2°C to 8°C).
- Keep the Prefilled Syringe in the original carton to protect it from light.
- Do not use the Prefilled Syringe that has been left in direct sunlight.
- Do not freeze the Prefilled Syringe. If the Prefilled Pen has been frozen, do not use the Prefilled Syringe even if it is thawed.
- Do not warm the Prefilled Syringe using heat sources such as hot water or a microwave. Let the Prefilled Syringe naturally warm at room temperature between 68°F to 77°F (20°C to 25°C) for 30 minutes before giving an injection.
- When the Prefilled Syringe has reached room temperature, do not put it back in the refrigerator. The Prefilled Syringe must be thrown away (discarded) if not used within the 14 days.
- Keep the Prefilled Syringe and all medicines out of the reach of children.

Prepare for the Injection

1. Gather the supplies for the injection.

1a. Prepare a clean, flat surface, such as a table or countertop, in a well-lit area.
1b. Remove 1 Prefilled Syringe from the carton by holding the middle of the Prefilled Syringe Body.

- Do not touch the plunger rod.

Note: Return the carton with any unused Prefilled Syringe to the refrigerator immediately after taking out one Prefilled Syringe.

1c. Make sure you have the following supplies:

- Prefilled Syringe
- Alcohol swab
Not included in the carton:
- Cotton ball or gauze
- Adhesive bandage
- FDA-cleared sharps disposal container

2. Inspect the Prefilled Syringe.

2a. Make sure you have the correct medicine (ZYMFENTRA).

2b. Check the expiration (EXP) date on label of the Prefilled Syringe (See Figure B).

2c. Look at the Prefilled Syringe and make sure it is not cracked or damaged.

- Do not use the Prefilled Syringe if:
  - it is cracked or damaged.
  - the expiration (EXP) date has passed.

Figure B

3. Inspect the Medicine.

3a. Look at the Prefilled Syringe Body and check the liquid is clear and colorless to pale brown (see Figure C).

- Do not use the Prefilled Syringe if the liquid is wrong color, cloudy, or contains particles in it.
- You may see air bubbles in the liquid. This is normal.

Figure C

4. Wait 30 minutes.

4a. Leave the Prefilled Syringe at room temperature 68°F to 77°F (20°C to 25°C) for 30 minutes to allow it to warm up (see Figure D).

- Do not warm the Prefilled Syringe using heat sources such as hot water or a microwave.

Figure D

5. Choose an injection site (see Figure E).

5a. You may inject into:

- the front of your thighs.

- the stomach area (abdomen) except for the 2 inches around the belly button (navel).

- the outer area of the upper arm (caregiver only).

- Do not inject into skin that is within 2 inches of your belly button (navel), or is red, hard, tender, damaged, bruised, or scarred.
- Do not inject through your clothes.

5b. Rotate the injection site each time you give an injection.

- Do not inject the same injection site each time you give an injection.
- Each new injection site should be at least 1.2 inches away from the previous injection site.

Figure E

6. Wash your hands.

6a. Wash your hands with soap and water and dry them thoroughly (see Figure F).

Figure F

7. Clean the injection site.

7a. Clean the injection site with an alcohol swab using a circular motion (see Figure G).
7b. Let the skin dry before injecting.

- Do not blow on or touch the injection site again before giving the injection.

Figure G

Give the injection

8. Remove the Cap.

8a. Hold the Prefilled Syringe by the injector body with the Cap on top using one hand. Gently pull the Cap straight off with the other hand.

- Do not pull back on plunger rod at any time.
- Do not remove the Cap until you are ready to inject.
- Do not try to put the Cap back onto the Prefilled Syringe.
- Do not touch the Needle.

8b. Throw away (dispose of) the Cap in an FDA cleared sharps container (see Step 12 and Figure H).

Figure H

9. Insert the Prefilled Syringe into the injection site.

9a. Hold the Prefilled Syringe by its body in one hand between your thumb and index finger.

9b. Gently pinch a fold of skin at the injection site with one hand.

9c. With a quick and “dart-like” motion, insert the Needle completely into the fold of the skin at a 45-defree angle (see Figure I).

- Do not change the position of the Prefilled Syringe after the injection has started.

Figure I

10. Give the injection.

10a. After the Needle is inserted, release the pinched skin.

10b. Push the Plunger down slowly and as far as it will go until the Prefilled Syringe is empty (See Figure J).

Figure J

11. Remove the Prefilled Syringe from the injection site.

11a. Remove the Needle from your skin at the same angle it was inserted (see Figure K).

- Do not reuse the Prefilled Syringe.
- Do not try to put the needle cover back on the Prefilled Syringe.
- Do not touch the Needle.
- Some bleeding may occur.
- Do not rub the injection site.

Figure K

After the injection

12. Throw away (dispose of) the Prefilled Syringe.

12a. Put the used Prefilled Syringe in an FDA-cleared sharps disposal container right away after use (see Figure L).

- Do not try to put the Cap back onto the Prefilled Syringe.
- Do not throw away (dispose of) the Prefilled Syringe in your household trash.
- If you do not have an FDA-cleared sharps disposal container, you may use a household container that is:
  - made of a heavy-duty plastic,
  - able to close with a tight-fitting, puncture-resistant lid, without sharps being able to come out,
  - upright and stable during use,
  - leak-resistant, and
  - properly labeled to warn of hazardous waste inside the container.
- When your sharps disposal container is almost full, you will need to follow your community guidelines for right way to disposal of it. There may be state or local laws about how you should throw away used needles and syringes. For more information about safe sharps disposal, and for specific information about sharps disposal in the state that you live in, go to the FDA's website at: http://www.fda.gov/safesharpsdisposal.
- Do not dispose of your sharps disposal container in your household trash unless your community guidelines permit this. Do not recycle your used sharps disposal container.

Figure L

13. Care for the injection site.

13a. Treat the injection site by gently pressing a cotton ball or gauze to the site and apply an adhesive bandage, if necessary.

Manufactured by: CELLTRION, Inc., 23, Academy-ro, Yeonsu-gu, Incheon, 22014, Republic of Korea
US License Number 1996

Distributed by: CELLTRION USA, Inc., 1 Evertrust Plaza Suite 1207, Jersey City, NJ 07302

INSTRUCTIONS FOR USE ZYMFENTRA (Zim fen' trah) (infliximab-dyyb) Injection for subcutaneous use only Single-Dose Prefilled Syringe with Needle Guard 120 mg/mL Rx Only

Read and follow the Instructions for Use that come with your ZYMFENTRA Prefilled Syringe before you start using it and each time you get a refill. There may be new information. This information dose not take the place of talking to your healthcare provider about your medical condition or treatment.

Figure A: Parts of Prefilled Syringe

Caution! Do not remove the Cap until you are ready to inject. Once you remove the Cap, do not recap the Syringe.

Important Information

- Use the Prefilled Syringe only if your healthcare provider has trained you on the right way to prepare for and to give an injection.
- Ask your healthcare provider how often you will need to give an injection.
- Rotate the injection site each time you give an injection. Each new injection site should be at least 1.2 inches away from the previous injection site.
- Do not use Prefilled Syringe if it has been dropped or is visibly damaged.
- Do not reuse the Prefilled Syringe.
- Do not shake the Prefilled Syringe at any time.
- Do not share the Prefilled Syringe with anyone.
- Do not pull back on the plunger rod at any time.
- Only use each Prefilled Syringe for one injection.

How to store the Prefilled Syringe

- Store the Prefilled Syringe in a refrigerator between 36°F to 46°F (2°C to 8°C).
- Keep the Prefilled Syringe in the original carton until use to protect it from light.
- Do not use the Prefilled Syringe that has been left in direct sunlight.
- Do not freeze the Prefilled Syringe. If the Prefilled Pen has been frozen, do not use the Prefilled Syringe even if it is thawed.
- Do not warm the Prefilled Syringe using heat sources such as hot water or a microwave. Let the Prefilled Syringe naturally warm at room temperature between 68°F to 77°F (20°C to 25°C) for 30 minutes before giving an injection.
- When the Prefilled Syringe has reached room temperature, do not put it back in the refrigerator. The Prefilled Syringe must be thrown away (discarded) if not used within the 14 days.
- Keep the Prefilled Syringe and all medicines out of the reach of children.

Prepare for the Injection

1. Gather the supplies for the injection.

1a. Prepare a clean, flat surface, such as a table or countertop, in a well-lit area.
1b. Remove 1 Prefilled Syringe from the carton by holding the middle of the Prefilled Syringe Body.

- Do not touch the plunger rod.

Note: Return the carton with any unused Prefilled Syringe to the refrigerator immediately after taking out one Prefilled Syringe.

1c. Make sure you have the following supplies:

- Prefilled Syringe
- Alcohol swab
Not included in the carton:
- Cotton ball or gauze
- Adhesive bandage
- FDA-cleared sharps disposal container

2. Inspect the Prefilled Syringe.

2a. Make sure you have the correct medicine (ZYMFENTRA).

2b. Check the expiration (EXP) date on the label of the Prefilled Syringe (See Figure B).

2c. Look at the Prefilled Syringe and make sure it is not cracked or damaged.

- Do not use the Prefilled Syringe if:
  - it is cracked or damaged.
  - the expiration (EXP) date has passed.

Figure B

3. Inspect the Medicine.

3a. Look through the Viewing Window and check that the liquid is clear and colorless to pale brown, and free of particles (see Figure C).

- Do not use the Prefilled Syringe if the liquid is wrong color, cloudy, or contains particles in it.
- You may see air bubbles in the liquid. This is normal.

Figure C

4. Wait 30 minutes.

4a. Leave the Prefilled Syringe at room temperature 68°F to 77°F (20°C to 25°C) for 30 minutes to allow it to warm up (see Figure D).

- Do not warm the Prefilled Syringe using heat sources such as hot water or a microwave.

Figure D

5. Choose an injection site (see Figure E).

5a. You may inject into:

- the front of your thighs.

- the stomach area (abdomen) except for the 2 inches around the belly button (navel).

- the outer area of the upper arm (caregiver only).

- Do not inject into skin that is within 2 inches of your belly button (navel), or is red, hard, tender, damaged, bruised, or scarred.
- Do not inject through your clothes.

5b. Rotate the injection site each time you give an injection.

- Do not injection the same injection site each time you five an injection.
- Each new injection site should be at least 1.2 inches away from the previous injection site.

Figure E

6. Wash your hands.

6a. Wash your hands with soap and water and dry them thoroughly (see Figure F).

Figure F

7. Clean the injection site.

7a. Clean the injection site with an alcohol swab (see Figure G).
7b. Let the skin dry before injecting.

- Do not blow on or touch the injection site again before giving the injection.

Figure G

Give the injection

8. Remove the Cap.

8a. Hold the Prefilled Syringe by the injector body with the Cap on top using one hand. Gently pull the Cap straight off with the other hand.

- Do not pull back on plunger rod at any time.
- Do not remove the Cap until you are ready to inject.
- Do not try to put the Cap back onto the Prefilled Syringe.
- Do not touch the Needle.

8b. Throw away (dispose of) the Cap in an FDA cleared sharps container (see Step 12 and Figure H).

Figure H

9. Insert the Prefilled Syringe into the injection site.

9a. Hold the Prefilled Syringe by its body in one hand between your thumb and index finger.

9b. Gently pinch a fold of skin at the injection site with one hand.

9c. Witha quick and “dart-like” motion, insert the Needle completely into the fold of the skin at a 45-defree angle (see Figure I).

Ÿ Do not change the position of the Prefilled Syringe after the injection has started.

Figure I

10. Give the injection.

10a. After the Needle is inserted, release the pinched skin.

10b. Push the Plunger down slowly and as far as it will go until the Prefilled Syringe is empty (See Figure J).

Note: The Needle Guard will not activate unless all the Medicines is injected.

Figure J

11. Remove the Prefilled Syringe from the injection site.

11a. After the Prefilled Syringe is empty, slowly lift your thumb from the Plunger until Needle is completely covered by the Neeld Guard (see Figure K).

- Do not reuse the Prefilled Syringe.
- Do not touch the Needle.
- Some bleeding may occur.
- Do not rub the injection site.

Figure K

After the injection

12. Throw away (dispose of) the Prefilled Syringe.

12a. Put the used Prefilled Syringe in an FDA-cleared sharps disposal container immediately after use (see Figure L).

- Do not try to put the Cap back onto the Prefilled Syringe.
- Do not throw away (dispose of) the Prefilled Syringe in your household trash.
- If you do not have an FDA-cleared sharps disposal container, you may use a household container that is:

- made of a heavy-duty plastic,
- able to closed with a tight-fitting, puncture-resistant lid, without sharps being able to come out,
- upright and stable during use,
- leak-resistant, and
- properly labeled to warn of hazardous waste inside the container.

- When your sharps disposal container is almost full, you will need to follow your community guidelines for the right way to disposal of it. There may be state or local laws about how you should throw away used needles and syringes. For more information about safe sharps disposal, and for specific information about sharps disposal, and for specific information about sharps disposal in the state that you live in, go to the FDA's website at: http://www.fda.gov/safesharpsdisposal.
- Do not dispose of your sharps disposal container in your household trash unless your community guidelines permit this. Do not recycle your used sharps disposal container.

Figure L

13. Care for the injection site.

13a. Treat the injection site by gently pressing a cotton ball or gauze to the site and apply an adhesive bandage, if necessary.

Manufactured by: CELLTRION, Inc., 23, Academy-ro, Yeonsu-gu, Incheon, 22014, Republic of Korea
US License Number 1996

Distributed by: CELLTRION USA, Inc., 1 Evertrust Plaza Suite 1207, Jersey City, NJ 07302

PRINCIPAL DISPLAY PANEL - 120 mg/mL Prefilled Pen Label

NDC 72606-025-01
Rx only

ZymfentraTM
infliximab–dyyb
injection
Subcutaneous use

CELLTRION Inc.

PRINCIPAL DISPLAY PANEL - 120 mg/mL Prefilled Pen Carton

ZymfentraTM

infliximab-dyyb
Injection
120 mg/mL

FOR SUBCUTANEOUS USE ONLY

ATTENTION: Disponse the enclosed Medication Guide to each patient.

NDC 72606-025-01

Rx ony

1 prefilled pen + 2 alcohol preps

1 Single-Dose Prefilled Pen

CELLTRION USA, Inc.

PRINCIPAL DISPLAY PANEL - 120 mg/mL Prefilled Syringe with Needle Guard Label

NDC 72606-025-09
Rx only

ZymfentraTM
infliximab–dyyb
injection
Subcutaneous use

CELLTRION, Inc.

PRINCIPAL DISPLAY PANEL - 120 mg/mL Prefilled Syringe with Needle Guard Carton

ZymfentraTM

infliximab-dyyb
injection
120 mg/mL

FOR SUBCUTANEOUS USE ONLY

ATTENTION: Dispense the enclosed Medication Guide to each patient.

NDC 72606-025-09

1 prefilled syringe with needle guard
+ 2 alcohol preps

1 Single-Dose Prefilled Syringe with Needle Guard

CELLTRION USA, Inc.

PRINCIPAL DISPLAY PANEL - 120 mg/mL Prefilled Syringe Label

NDC 72606-025-05
Rx only

ZymfentraTM
infliximab–dyyb
injection
Subcutaneous use

CELLTRION, Inc.

PRINCIPAL DISPLAY PANEL - 120 mg/mL Prefilled Syringe Carton

ZymfentraTM

infliximab-dyyb
injection
120 mg/mL

FOR SUBCUTANEOUS USE ONLY

ATTENTION: Dispense the enclosed Medication Guide to each patient.

NDC x72606-025-05

Rx

1 prefilled syringe + 2 alcohol preps

1 Single-Dose Prefilled Syringe
CELLTRION USA, Inc.